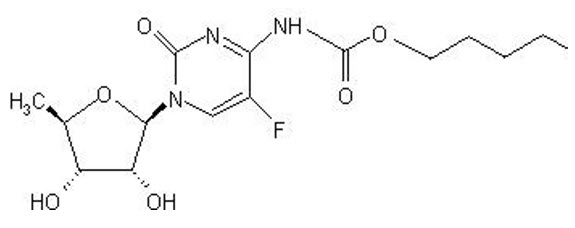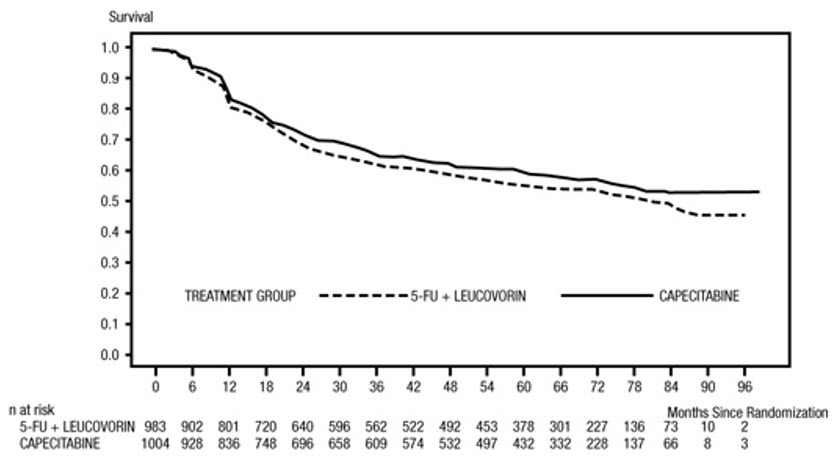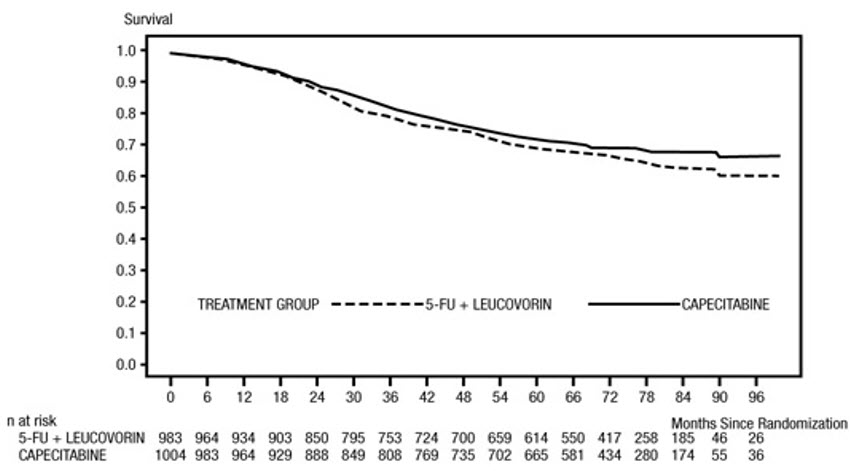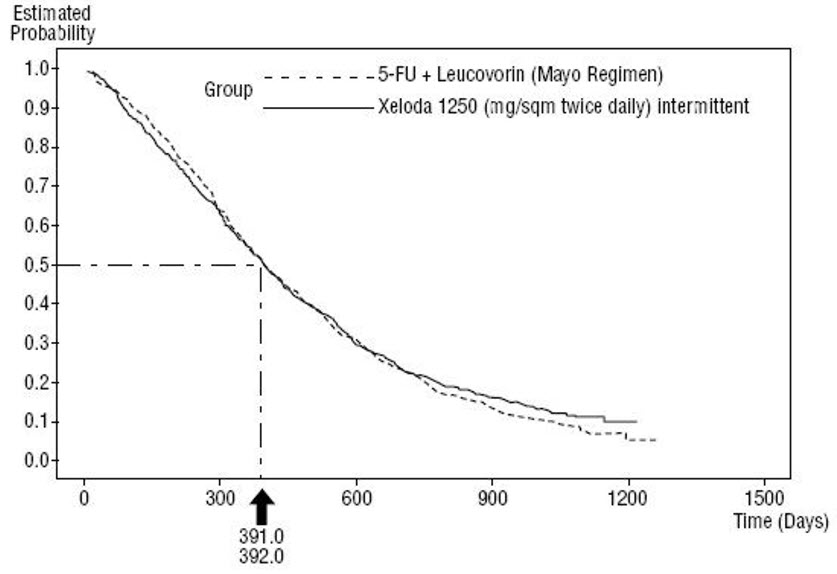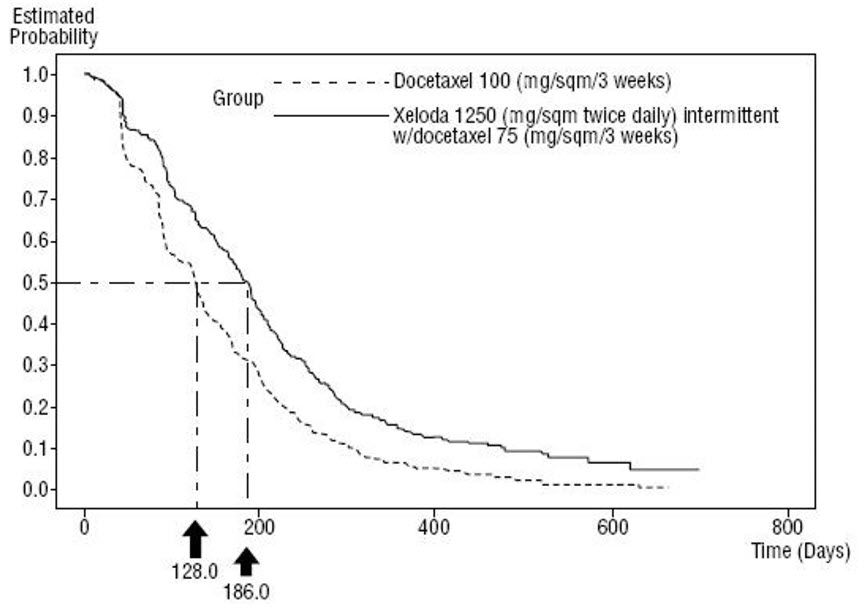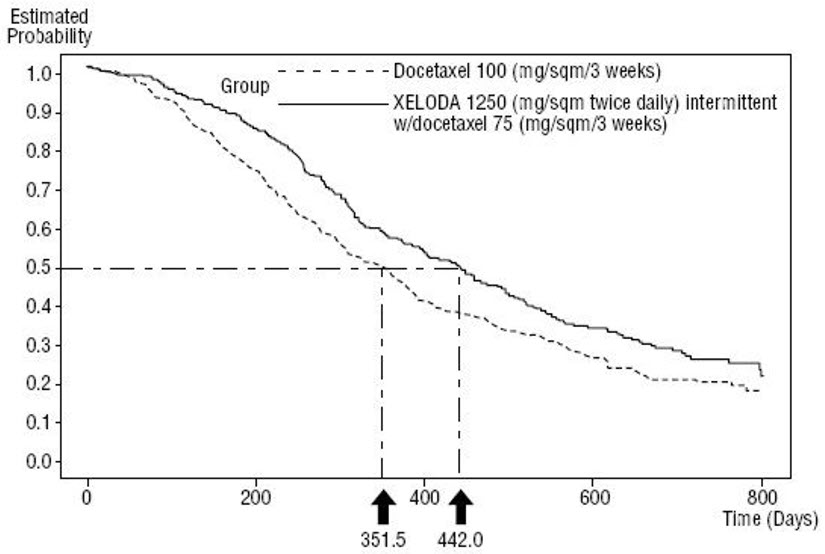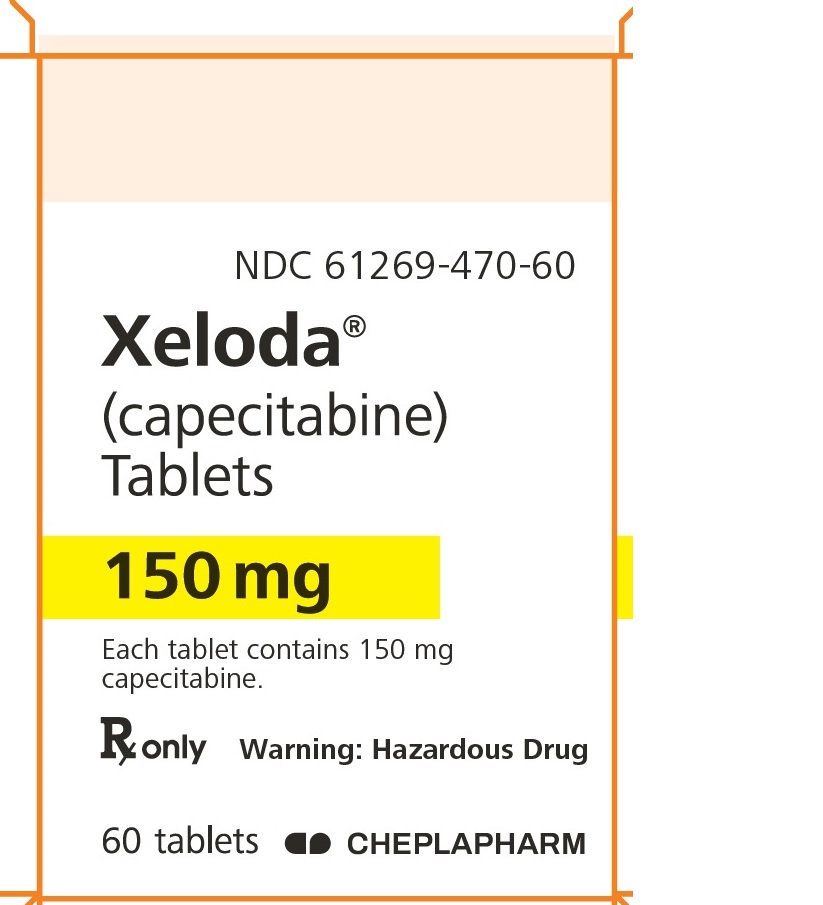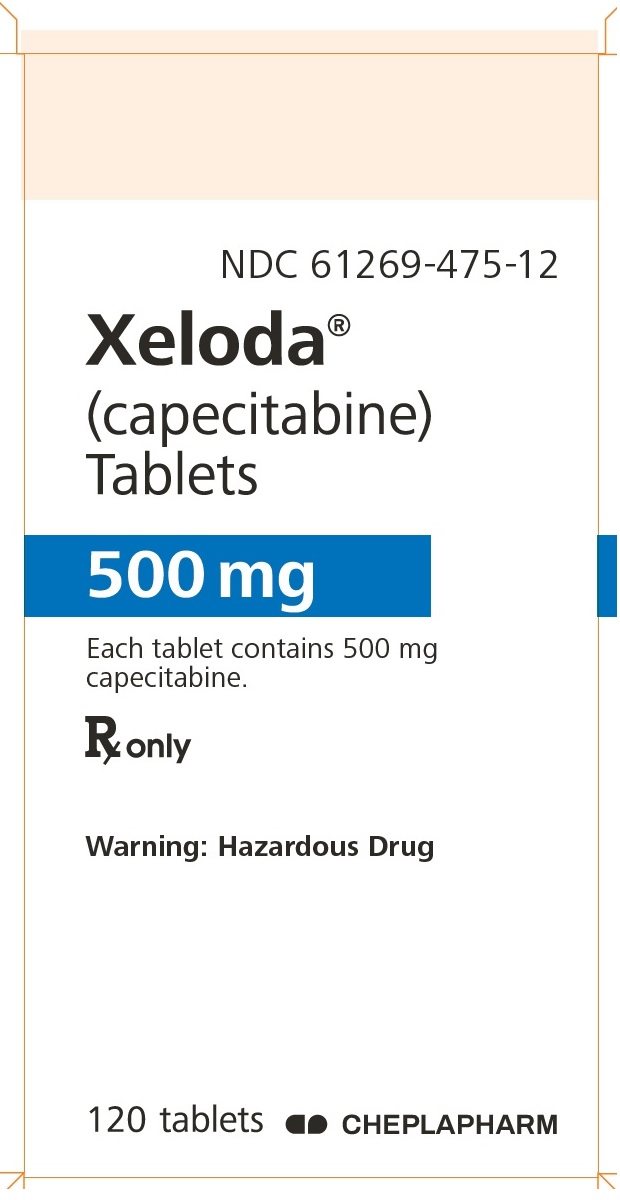 DRUG LABEL: XELODA
NDC: 61269-470 | Form: TABLET, FILM COATED
Manufacturer: H2-Pharma, LLC
Category: prescription | Type: HUMAN PRESCRIPTION DRUG LABEL
Date: 20260205

ACTIVE INGREDIENTS: CAPECITABINE 150 mg/1 1
INACTIVE INGREDIENTS: CROSCARMELLOSE SODIUM; ANHYDROUS LACTOSE; HYPROMELLOSE 2910 (6 MPA.S); HYPROMELLOSE 2208 (3 MPA.S); MICROCRYSTALLINE CELLULOSE; MAGNESIUM STEARATE; TALC; TITANIUM DIOXIDE; FERRIC OXIDE RED; FERRIC OXIDE YELLOW

HIGHLIGHTS OF PRESCRIBING INFORMATION

These highlights do not include all the information needed to use XELODA® safely and effectively. See full prescribing information for XELODA®.
XELODA® (capecitabine) tablets, for oral use
Initial U.S. Approval: 1998

WARNING: SERIOUS ADVERSE REACTIONS OR DEATH IN PATIENTS WITH COMPLETE DPD DEFICIENCY and INCREASED RISK OF BLEEDING WITH CONCOMITANT USE OF VITAMIN K ANTAGONISTS

WARNING: SERIOUS ADVERSE REACTIONS OR DEATH IN PATIENTS WITH COMPLETE DPD DEFICIENCY and BLEEDING WITH CONCOMITANT USE OF VITAMIN K ANTAGONISTS

See full prescribing information for complete boxed warning.

Serious adverse reactions or death may occur in patients with complete DPD deficiency. Test patients for genetic variants of DPYD prior to initiating XELODA unless immediate treatment is necessary. Avoid use of Xeloda in patients with certain homozygous or compound heterozygous DPYD variants that result in complete DPD deficiency. (5.1)

Altered coagulation parameters and/or bleeding, including death, have been reported in patients taking XELODA concomitantly with oral vitamin K antagonists. (5.2, 7.2)

Monitor international normalized ratio (INR) more frequently and adjust the dose of the vitamin K antagonist as appropriate. (7.2)

RECENT MAJOR CHANGES

Boxed Warning | (10/2025)
Dosage and Administration (2.1) | (10/2025)
Warnings and Precautions (5.1) | (10/2025)

1 INDICATIONS AND USAGE

XELODA (capecitabine) is a nucleoside metabolic inhibitor indicated for:

Colorectal Cancer

- adjuvant treatment of patients with Stage III colon cancer as a single agent or as a component of a combination chemotherapy regimen. (1.1)
- perioperative treatment of adults with locally advanced rectal cancer as a component of chemoradiotherapy. (1.1)
- treatment of patients with unresectable or metastatic colorectal cancer as a single agent or as a component of a combination chemotherapy regimen. (1.1)

Breast Cancer

- treatment of patients with advanced or metastatic breast cancer as a single agent if an anthracycline- or taxane-containing chemotherapy is not indicated. (1.2)
- treatment of patients with advanced or metastatic breast cancer in combination with docetaxel after disease progression on prior anthracycline-containing chemotherapy. (1.2)

Gastric, Esophageal, or Gastroesophageal Junction Cancer

- treatment of adults with unresectable or metastatic gastric, esophageal, or gastroesophageal junction cancer as a component of a combination chemotherapy regimen. (1.3)
- treatment of adults with HER2-overexpressing metastatic gastric or gastroesophageal junction adenocarcinoma who have not received prior treatment for metastatic disease as a component of a combination regimen. (1.3)

Pancreatic Cancer

- adjuvant treatment of adults with pancreatic adenocarcinoma as a component of a combination chemotherapy regimen. (1.4)

2 DOSAGE AND ADMINISTRATION

Adjuvant Treatment of Colon Cancer

- Single agent: 1,250 mg/m^2 twice daily orally for the first 14 days of each 21-day cycle for a maximum of 8 cycles. (2.1) In combination with Oxaliplatin-Containing Regimens: 1,000 mg/m^2 orally twice daily for the first 14 days of each 21-day cycle for a maximum of 8 cycles in combination with oxaliplatin 130 mg/m^2 administered intravenously on day 1 of each cycle. (2.1)

Perioperative Treatment of Rectal Cancer

- With Concomitant Radiation Therapy: 825 mg/m^2 orally twice daily (2.2)
- Without Radiation Therapy: 1,250 mg/m^2 orally twice daily (2.2)

Unresectable or Metastatic Colorectal Cancer:

- Single agent: 1,250 mg/m^2 twice daily orally for the first 14 days of each 21-day cycle until disease progression or unacceptable toxicity. (2.2)
- In Combination with Oxaliplatin: 1,000 mg/m^2 orally twice daily for the first 14 days of each 21-day cycle until disease progression or unacceptable toxicity in combination with oxaliplatin 130 mg/m^2 administered intravenously on day 1 of each cycle. (2.2)

Advanced or Metastatic Breast Cancer:

- Single agent: 1,000 mg/m^2 or 1,250 mg/m^2 twice daily orally for the first 14 days of each 21-day cycle until disease progression or unacceptable toxicity. (2.3)
- In combination with docetaxel: 1,000 mg/m^2 or 1,250 mg/m^2 orally twice daily for the first 14 days of a 21-day cycle, until disease progression or unacceptable toxicity in combination with docetaxel at 75 mg/m^2 administered intravenously on day 1 of each cycle (2.3)

Unresectable or Metastatic Gastric, Esophageal, or Gastroesophageal Junction Cancer

- 625 mg/m^2 orally twice daily on days 1 to 21 of each 21-day cycle for a maximum of 8 cycles in combination with platinum-containing chemotherapy. (2.4)
  OR
- 850 mg/m^2 or 1,000 mg/m^2 orally twice daily for the first 14 days of each 21-day cycle until disease progression or unacceptable toxicity in combination with oxaliplatin 130 mg/m^2 administered intravenously on day 1 of each cycle. (2.4)

HER2-overexpressing metastatic adenocarcinoma of the gastroesophageal junction or stomach

- 1,000 mg/m^2 orally twice daily for the first 14 days of each 21-day cycle until disease progression or unacceptable toxicity in combination with cisplatin and trastuzumab. (2.4)

Pancreatic cancer

- 830 mg/m^2 orally twice daily for the first 21 days of each 28-day cycle for maximum of 6 cycles in combination with gemcitabine 1,000 mg/m^2 administered intravenously on days 1, 8, and 15 of each cycle. (2.5)

Refer to Sections 2.5 and 2.6 for information related to dosage modifications for adverse reactions and renal impairment (2.5 and 2.6).

3 DOSAGE FORMS AND STRENGTHS

Tablets: 150 mg and 500 mg (3)

4 CONTRAINDICATIONS

History of severe hypersensitivity reactions to fluorouracil or capecitabine (4)

5 WARNINGS AND PRECAUTIONS

- Cardiotoxicity: May be more common in patients with a prior history of coronary artery disease. Withhold XELODA for cardiotoxicity as appropriate. The safety of resumption of XELODA in patients with cardiotoxicity that has resolved has not been established. (2.5, 5.3)
- Diarrhea: Withhold XELODA and then resume at same or reduced dose, or permanently discontinue, based on severity and occurrence. (2.5, 5.4)
- Dehydration: Optimize hydration before starting XELODA. Monitor hydration status and kidney function at baseline and as clinically indicated. Withhold XELODA and then resume at same or reduced dose, or permanently discontinue, based on severity and occurrence. (2.5, 5.5)
- Renal Toxicity: Monitor renal function at baseline and as clinically indicated. Optimize hydration before starting XELODA. Withhold XELODA and then resume at same or reduced dose, or permanently discontinue, based on severity and occurrence. (2.5, 5.6)
- Serious Skin Toxicities: Monitor for new or worsening serious skin reactions. Permanently discontinue XELODA in patients who experience a severe cutaneous adverse reaction. (5.7)
- Palmar-Plantar Erythrodysesthesia Syndrome: Withhold XELODA then resume at same or reduced dose, or permanently discontinue, based on severity and occurrence. (2.5, 5.8)
- Myelosuppression: Monitor complete blood count at baseline and before each cycle. XELODA is not recommended in patients with baseline neutrophil counts <1.5 × 10^9/L or platelet counts <100 × 10^9/L. For grade 3 or 4 myelosuppression, withhold XELODA and then resume at same or reduced dose, or permanently discontinue, based on occurrence. (2.5, 5.9)
- Hyperbilirubinemia: Patients with Grade 3-4 hyperbilirubinemia may resume treatment once the event is Grade 2 or less (≤3 × ULN), using the percent of current dose as shown in column 3 of Table 1 (2.5, 5.10)
- Embryo-Fetal Toxicity: Can cause fetal harm. Advise patients of the potential risk to a fetus and to use effective contraception. (5.11, 8.1, 8.3)

6 ADVERSE REACTIONS

- Most common adverse reactions in patients who received XELODA as a single agent for the adjuvant treatment for colon cancer (≥30%) were palmar-plantar erythrodysesthesia syndrome, diarrhea, and nausea. (6.1)
- Most common adverse reactions (≥30%) in patients with metastatic colorectal cancer who received XELODA as a single agent were anemia, diarrhea, palmar-plantar erythrodysesthesia syndrome, hyperbilirubinemia, nausea, fatigue, and abdominal pain. (6.1)
- Most common adverse reactions (≥30%) in patients with metastatic breast cancer who received XELODA with docetaxel were diarrhea, stomatitis, palmar-plantar erythrodysesthesia syndrome, nausea, alopecia, vomiting, edema, and abdominal pain. (6.1)
- Most common adverse reactions (≥30%) in patients with metastatic breast cancer who received XELODA as a single agent were lymphopenia, anemia, diarrhea, hand-and-foot syndrome, nausea, fatigue, vomiting, and dermatitis. (6.1)

To report SUSPECTED ADVERSE REACTIONS, contact 1-866-995-4272 or FDA at 1-800-FDA-1088 or www.fda.gov/medwatch.

7 DRUG INTERACTIONS

- Allopurinol: Avoid concomitant use of allopurinol with XELODA. (7.1)
- Leucovorin: Closely monitor for toxicities when XELODA is coadministered with leucovorin. (7.1)
- CYP2C9 substrates: Closely monitor for adverse reactions when CYP2C9 substrates are coadministered with XELODA. (7.2)
- Vitamin K antagonists: Monitor INR more frequently and dose adjust oral vitamin K antagonist as appropriate
- Phenytoin: Closely monitor phenytoin levels in patients taking XELODA concomitantly with phenytoin and adjust the phenytoin dose as appropriate. (7.2)
- Nephrotoxic drugs: Closely monitor for signs of renal toxicity when XELODA is used concomitantly with nephrotoxic drugs. (7.3)

8 USE IN SPECIFIC POPULATIONS

- Lactation: Advise not to breastfeed. (8.2)
- Hepatic Impairment: Monitor patients with hepatic impairment more frequently for adverse reactions. (8.7)

FULL PRESCRIBING INFORMATION

WARNING: SERIOUS ADVERSE REACTIONS OR DEATH IN PATIENTS WITH COMPLETE DPD DEFICIENCY and INCREASED RISK OF BLEEDING WITH CONCOMITANT USE OF VITAMIN K ANTAGONISTS

Increased risk of serious adverse reactions or death in patients with complete DPD deficiency
• Test patients for genetic variants of DPYD prior to initiating XELODA unless immediate treatment is necessary. Avoid use of XELODA in patients with certain homozygous or compound heterozygous DPYD variants that result in complete DPD deficiency [see Warnings and Precautions (5.1)].
Increased risk of bleeding with concomitant use of Vitamin K antagonists
• Altered coagulation parameters and/or bleeding, including death, have been reported in patients taking XELODA concomitantly with oral vitamin K antagonists, such as warfarin [see Warnings and Precautions (5.2), Drug Interactions (7.2)].
• Clinically significant increases in prothrombin time (PT) and international normalized ratio (INR) have been reported in patients who were on stable doses of a vitamin K antagonist at the time XELODA was introduced. These events occurred in patients with and without liver metastases.
• Monitor INR more frequently and adjust the dose of the vitamin K antagonist as appropriate [see Drug Interactions (7.2)].

1 INDICATIONS AND USAGE

1.1 Colorectal Cancer

XELODA is indicated for the:

- adjuvant treatment of patients with Stage III colon cancer as a single agent or as a component of a combination chemotherapy regimen.
- perioperative treatment of adults with locally advanced rectal cancer as a component of chemoradiotherapy.
- treatment of patients with unresectable or metastatic colorectal cancer as a single agent or as a component of a combination chemotherapy regimen.

1.2 Breast Cancer

XELODA is indicated for the:

- treatment of patients with advanced or metastatic breast cancer as a single agent if an anthracycline- or taxane-containing chemotherapy is not indicated.
- treatment of patients with advanced or metastatic breast cancer in combination with docetaxel after disease progression on prior anthracycline-containing chemotherapy.

1.3 Gastric, Esophageal, or Gastroesophageal Junction Cancer

XELODA is indicated for the:

- treatment of adults with unresectable or metastatic gastric, esophageal, or gastroesophageal junction cancer as a component of a combination chemotherapy regimen.
- treatment of adults with HER2-overexpressing metastatic gastric or gastroesophageal junction adenocarcinoma who have not received prior treatment for metastatic disease as a component of a combination regimen.

1.4 Pancreatic Cancer

XELODA is indicated for the adjuvant treatment of adults with pancreatic adenocarcinoma as a component of a combination chemotherapy regimen.

2 DOSAGE AND ADMINISTRATION

2.1 Evaluation and Testing for DPD Deficiency Before Initiating XELODA

Prior to initiating XELODA, test patients for genetic variants of the DPYD gene unless immediate treatment is necessary. An FDA-authorized test for the detection of the DPYD gene to identify patients at risk of serious adverse reactions with XELODA is not currently available. Currently available tests used to identify DPYD variants may vary in accuracy and design (e.g., which DPYD variant(s) they identify).

Avoid use of XELODA in patients known to have certain homozygous or compound heterozygous DPYD variants that result in complete DPD deficiency. No XELODA dose has been proven safe for patients with complete DPD deficiency. For patients with partial DPD deficiency, individualize the dosage and modify based on tolerability and intent of treatment [see Warnings and Precautions (5.1)].

2.2 Recommended Dosage for Colorectal Cancer

Adjuvant Treatment of Colon Cancer

Single Agent

The recommended dosage of XELODA is 1,250 mg/m^2 orally twice daily for the first 14 days of each 21-day cycle for a maximum of 8 cycles.

In Combination with Oxaliplatin-Containing Regimens

The recommended dosage of XELODA is 1,000 mg/m^2 orally twice daily for the first 14 days of each 21-day cycle for a maximum of 8 cycles in combination with oxaliplatin 130 mg/m^2 administered intravenously on day 1 of each cycle.

Refer to the oxaliplatin prescribing information for additional dosing information as appropriate.

Perioperative Treatment of Rectal Cancer

The recommended dosage of capecitabine is 825 mg/m^2 orally twice daily when administered with concomitant radiation therapy and 1,250 mg/m^2 orally twice daily when administered without radiation therapy as part of a peri-operative combination regimen.

Unresectable or Metastatic Colorectal Cancer

Single Agent

The recommended dosage of XELODA is 1,250 mg/m^2 orally twice daily for the first 14 days of a 21-day cycle until disease progression or unacceptable toxicity.

In Combination with Oxaliplatin

The recommended dosage of XELODA is 1,000 mg/m^2 orally twice daily for the first 14 days of each 21-day cycle until disease progression or unacceptable toxicity in combination with oxaliplatin 130 mg/m^2 administered intravenously on day 1 of each cycle.

Refer to the Prescribing Information for oxaliplatin for additional dosing information as appropriate.

2.3 Recommended Dosage for Breast Cancer

Advanced or Metastatic Breast Cancer

Single Agent

The recommended dosage of XELODA is 1,000 mg/m^2 or 1,250 mg/m^2 orally twice daily for the first 14 days of a 21-day cycle until disease progression or unacceptable toxicity. Individualize the dose and dosing schedule of XELODA based on patient risk factors and adverse reactions.

In Combination with Docetaxel

The recommended dosage of XELODA is 1,000 mg/m^2 or 1,250 mg/m^2 orally twice daily for the first 14 days of a 21-day cycle until disease progression or unacceptable toxicity in combination with docetaxel 75 mg/m^2 administered intravenously on day 1 of each cycle.

Refer to the Prescribing Information for docetaxel for additional dosing information as appropriate.

2.4 Recommended Dosage for Gastric, Esophageal, or Gastroesophageal Junction Cancer

The recommended dosage of XELODA for unresectable or metastatic gastric, esophageal, or gastroesophageal junction cancer is:

- 625 mg/m^2 orally twice daily on days 1 to 21 of each 21-day cycle for a maximum of 8 cycles in combination with platinum-containing chemotherapy.
  OR
- 850 mg/m^2 or 1,000 mg/m^2 orally twice daily for the first 14 days of each 21-day cycle until disease progression or unacceptable toxicity in combination with oxaliplatin 130 mg/m^2 administered intravenously on day 1 of each cycle. Individualize the dose and dosing schedule of XELODA based on patient risk factors and adverse reactions.

The recommended dosage of XELODA for HER2-overexpressing metastatic gastric or gastroesophageal junction adenocarcinoma is 1,000 mg/m^2 orally twice daily for the first 14 days of each 21-day cycle until disease progression or unacceptable toxicity in combination with cisplatin and trastuzumab.

Refer to the Prescribing Information for agents used in combination for additional dosing information as appropriate.

2.5 Recommended Dosage for Pancreatic Cancer

The recommended dosage of XELODA is 830 mg/m^2 orally twice daily for the first 21 days of each 28-day cycle until disease progression, unacceptable toxicity, or for a maximum 6 cycles in combination with gemcitabine 1,000 mg/m^2 administered intravenously on days 1, 8, and 15 of each cycle.

Refer to Prescribing Information for gemcitabine for additional dosing information as appropriate.

2.6 Dosage Modifications for Adverse Reactions

Monitor patients for adverse reactions and modify dosages of XELODA as described in Table 1. Do not replace missed doses of XELODA; instead resume XELODA with the next planned dosage.

When XELODA is administered with docetaxel, withhold XELODA and docetaxel until the requirements for resuming both XELODA and docetaxel are met. Refer to the Prescribing Information for docetaxel for additional dosing information as appropriate.

Table 1 Recommended Dosage Modifications for Adverse Reactions
Severity | Dosage Modification | Resume at Same or Reduced Dose (Percent of Current Dose)
Grade 2
1st appearance | Withhold until resolved to grade 0-1. | 100%
2nd appearance | Withhold until resolved to grade 0-1. | 75%
3rd appearance | Withhold until resolved to grade 0-1. | 50%
4th appearance | Permanently discontinue. | -
Grade 3
1st appearance | Withhold until resolved to grade 0-1. | 75%
2nd appearance | Withhold until resolved to grade 0-1. | 50%
3rd appearance | Permanently discontinue. | -
Grade 4
1st appearance | Permanently discontinue OR Withhold until resolved to grade 0-1. | 50%

Hyperbilirubinemia

Patients with Grade 3-4 hyperbilirubinemia may resume treatment once the event is Grade 2 or less (less than three times the upper limit of normal), using the percent of current dose as shown in column 3 of Table 1 [see Warnings and Precautions (5.10)].

2.7 Dosage Modification For Renal Impairment

Reduce the dose of XELODA by 25% for patients with creatinine clearance (CLcr) of 30 to 50 mL/min as determined by Cockcroft-Gault equation. A dosage has not been established in patients with severe renal impairment (CLcr <30 mL/min) [see Use in Specific Populations (8.6)].

2.8 Administration

Round the recommended dosage for patients to the nearest 150 mg dose to provide whole XELODA tablets.

Swallow XELODA tablets whole with water within 30 minutes after a meal. Do not chew, cut, or crush XELODA tablets [see Warnings and Precautions (5.12)].

Take XELODA at the same time each day approximately 12 hours apart.

Do not take an additional dose after vomiting and continue with the next scheduled dose.

Do not take a missed dose and continue with the next scheduled dose.

XELODA is a hazardous drug. Follow applicable special handling and disposal procedures.^1

3 DOSAGE FORMS AND STRENGTHS

Tablets, film-coated:

- 150 mg: biconvex, oblong, light-peach colored, with "XELODA" on one side and "150" on the other
- 500 mg: biconvex, oblong, peach colored, with "XELODA on one side and "500" on the other

4 CONTRAINDICATIONS

XELODA is contraindicated in patients with history of severe hypersensitivity reaction to fluorouracil or capecitabine [see Adverse Reactions (6.1)].

5 WARNINGS AND PRECAUTIONS

5.1 Serious Adverse Reactions or Death from Dihydropyrimidine Dehydrogenase (DPD) Deficiency

Patients with certain homozygous or compound heterozygous variants in the DPYD gene known to result in complete or near complete absence of DPD activity (complete DPD deficiency) are at increased risk for acute early-onset toxicity and serious, including fatal, adverse reactions due to XELODA (e.g., mucositis, diarrhea, neutropenia, and neurotoxicity). Patients with partial DPD activity (partial DPD deficiency) may also have increased risk of serious or fatal, adverse reactions.

Prior to initiating XELODA, test patients for genetic variants of the DPYD gene unless immediate treatment is necessary [see Clinical Pharmacology (12.5)]. Serious adverse reactions may still occur even if no DPYD variants are identified.

Avoid use of XELODA in patients with certain homozygous or compound heterozygous DPYD variants that result in complete DPD deficiency.

Withhold or permanently discontinue XELODA based on clinical assessment of the onset, duration, and severity of adverse reactions in patients with evidence of acute early-onset or unusually severe reactions. No XELODA dose has been proven safe for patients with complete DPD deficiency. There are insufficient data to recommend a specific dose in patients with partial DPD deficiency. For patients with partial DPD deficiency, individualize the dosage and modify based on tolerability and intent of treatment.

An FDA-authorized test for the detection of genetic variants of the DPYD gene to identify patients at risk of serious adverse reactions with XELODA treatment is not currently available. Currently available tests used to identify DPYD variants may vary in accuracy and design (e.g., which DPYD variant(s) they identify).

5.2 Increased Risk of Bleeding With Concomitant Use of Vitamin K Antagonists

Altered coagulation parameters and/or bleeding, including death, have been reported in patients taking XELODA concomitantly with vitamin K antagonists, such as warfarin.

Clinically significant increases in PT and INR have been reported in patients who were on stable doses of oral vitamin K antagonists at the time XELODA was introduced. These events occurred within several days and up to several months after initiating XELODA and, in a few cases, within 1 month after stopping XELODA. These events occurred in patients with and without liver metastases.

Monitor INR more frequently and adjust the dose of the vitamin K antagonist as appropriate [see Drug Interactions (7.1)].

5.3 Cardiotoxicity

Cardiotoxicity can occur with XELODA. Myocardial infarction/ischemia, angina, dysrhythmias, cardiac arrest, cardiac failure, sudden death, electrocardiographic changes, and cardiomyopathy have been reported with XELODA. These adverse reactions may be more common in patients with a prior history of coronary artery disease.

Withhold XELODA for cardiotoxicity as appropriate [see Dosage and Administration (2.5)]. The safety of resumption of XELODA in patients with cardiotoxicity that has resolved have not been established.

5.4 Diarrhea

Diarrhea, sometimes severe, can occur with XELODA. In 875 patients with metastatic breast or colorectal cancer who received XELODA as a single agent, the median time to first occurrence of grade 2 to 4 diarrhea was 34 days (range: 1 day to 1 year). The median duration of grade 3 to 4 diarrhea was 5 days.

Withhold XELODA and then resume at same or reduced dose or permanently discontinue based on severity and occurrence [see Dosage and Administration (2.5)].

5.5 Dehydration

Dehydration can occur with XELODA. Patients with anorexia, asthenia, nausea, vomiting, or diarrhea may be at an increased risk of developing dehydration with XELODA. Optimize hydration before starting XELODA. Monitor hydration status and kidney function at baseline and as clinically indicated. Withhold XELODA and then resume at same or reduced dose, or permanently discontinue, based on severity and occurrence [see Dosage and Administration (2.5)].

5.6 Renal Toxicity

Serious renal failure, sometimes fatal, can occur with XELODA. Renal impairment or coadministration of XELODA with other products known to cause renal toxicity may increase the risk of renal toxicity [see Drug Interactions (7.3)].

Monitor renal function at baseline and as clinically indicated. Optimize hydration before starting XELODA. Withhold XELODA and then resume at same or reduced dose, or permanently discontinue, based on severity and occurrence [see Dosage and Administration (2.5)].

5.7 Serious Skin Toxicities

Severe cutaneous adverse reactions (SCARs), including Stevens-Johnson Syndrome and toxic epidermal necrolysis (TEN), which can be fatal, can occur with XELODA [see Adverse Reactions (6.2)].

Monitor for new or worsening serious skin reactions. Permanently discontinue XELODA for severe cutaneous adverse reactions.

5.8 Palmar-Plantar Erythrodysesthesia Syndrome

Palmar-plantar erythrodysesthesia syndrome (PPES) can occur with XELODA.

In patients with metastatic breast or colorectal cancer who received XELODA as a single agent, the median time to onset of grades 1 to 3 PPES was 2.6 months (range: 11 days to 1 year).

Withhold XELODA and then resume at same or reduced dose or permanently discontinue based on severity and occurrence [see Dosage and Administration (2.5)].

5.9 Myelosuppression

Myelosuppression can occur with XELODA.

In the 875 patients with metastatic breast or colorectal cancer who received XELODA as a single agent, 3.2% had grade 3 or 4 neutropenia, 1.7% had grade 3 or 4 thrombocytopenia, and 2.4% had grade 3 or 4 anemia.

In the 251 patients with metastatic breast cancer who received XELODA with docetaxel, 68% had grade 3 or 4 neutropenia, 2.8% had grade 3 or 4 thrombocytopenia, and 10% had grade 3 or 4 anemia.

Necrotizing enterocolitis (typhlitis) has been reported. Consider typhlitis in patients with fever, neutropenia and abdominal pain.

Monitor complete blood count at baseline and before each cycle. XELODA is not recommended if baseline neutrophil count <1.5 × 10^9/L or platelet count <100 × 10^9/L. For grade 3 to 4 myelosuppression, withhold XELODA and then resume at same or reduced dose, or permanently discontinue, based on occurrence [see Dosage and Administration (2.5)].

5.10 Hyperbilirubinemia

Hyperbilirubinemia can occur with XELODA. In the 875 patients with metastatic breast or colorectal cancer who received XELODA as a single agent, grade 3 hyperbilirubinemia occurred in 15% of patients and grade 4 hyperbilirubinemia occurred in 3.9%. Of the 566 patients who had hepatic metastases at baseline and the 309 patients without hepatic metastases at baseline, grade 3 or 4 hyperbilirubinemia occurred in 23% and 12%, respectively. Of these 167 patients with grade 3 or 4 hyperbilirubinemia, 19% had postbaseline increased alkaline phosphatase and 28% had postbaseline increased transaminases at any time (not necessarily concurrent). The majority of these patients with increased transaminases or alkaline phosphatase had liver metastases at baseline. In addition, 58% and 35% of the 167 patients with grade 3 or 4 hyperbilirubinemia had pre- and postbaseline increased alkaline phosphatase or transaminases (grades 1 to 4), respectively. Only 8% (n=13) and 3% (n=5) had grade 3 or 4 increased alkaline phosphatase or transaminases.

In the 596 patients who received XELODA for metastatic colorectal cancer, the incidence of grade 3 or 4 hyperbilirubinemia was similar to that observed for the pooled population of patients with metastatic breast and colorectal cancer. The median time to onset for grade 3 or 4 hyperbilirubinemia was 64 days and median total bilirubin increased from 8 µm/L at baseline to 13 µm/L during treatment with XELODA. Of the 136 patients with grade 3 or 4 hyperbilirubinemia, 49 patients had grade 3 or 4 hyperbilirubinemia as their last measured value, of which 46 had liver metastases at baseline.

In the 251 patients with metastatic breast cancer who received XELODA with docetaxel, grade 3 hyperbilirubinemia occurred in 7% and grade 4 hyperbilirubinemia occurred in 2%.

Withhold XELODA and then resume at a same or reduced dose, or permanently discontinue, based on occurrence [see Dosage and Administration (2.5)]. Patients with Grade 3-4 hyperbilirubinemia may resume treatment once the event is Grade 2 or less than three times the upper limit of normal, using the percent of current dose as shown in Table 1 [see Dosage and Administration (2.5)].

5.11 Embryo-Fetal Toxicity

Based on findings from animal reproduction studies and its mechanism of action, XELODA can cause fetal harm when administered to a pregnant woman. Insufficient data is available on XELODA use in pregnant women to evaluate a drug-associated risk. In animal reproduction studies, administration of capecitabine to pregnant animals during the period of organogenesis caused embryolethality and teratogenicity in mice and embryolethality in monkeys at 0.2 and 0.6 times the human exposure (AUC) in patients who received a dosage of 1,250 mg/m^2 twice daily, respectively.

Advise pregnant women of the potential risk to a fetus. Advise females of reproductive potential to use effective contraception during treatment with XELODA and for 6 months following the last dose. Advise males with female partners of reproductive potential to use effective contraception during treatment with XELODA and for 3 months following the last dose [see Use in Specific Populations (8.1, 8.3)].

5.12 Eye Irritation, Skin Rash, and Other Adverse Reactions from Exposure to Crushed Tablets

In instances of exposure to crushed XELODA tablets, the following adverse reactions have been reported: eye irritation and swelling, skin rash, diarrhea, paresthesia, headache, gastric irritation, vomiting and nausea. Advise patients not to cut or crush tablets.

If XELODA tablets must be cut or crushed, this should be done by a professional trained in safe handling of cytotoxic drugs using appropriate equipment and safety procedures [see Dosage and Administration (2.7)]. The safety and effectiveness have not been established for the administration of crushed XELODA tablets.

6 ADVERSE REACTIONS

The following clinically significant adverse reactions are described elsewhere in the labeling:

- Cardiotoxicity [see Warnings and Precautions (5.3)]
- Diarrhea [see Warnings and Precautions (5.4)]
- Dehydration [see Warnings and Precautions (5.5)]
- Renal Toxicity [see Warnings and Precautions (5.6)]
- Serious Skin Toxicities [see Warnings and Precautions (5.7)]
- Palmar-Plantar Erythrodysesthesia Syndrome [see Warnings and Precautions (5.8)]
- Myelosuppression [see Warnings and Precautions (5.9)]
- Hyperbilirubinemia [see Warnings and Precautions (5.10)]

6.1 Clinical Trials Experience

Because clinical trials are conducted under widely varying conditions, adverse reaction rates observed in the clinical trials of a drug cannot be directly compared to rates in the clinical trials of another drug and may not reflect the rates observed in practice.

Adjuvant Treatment of Colon Cancer

Single Agent

The safety of XELODA as a single agent was evaluated in patients with Stage III colon cancer in X-ACT [see Clinical Studies (14.1)]. Patients received XELODA 1,250 mg/m^2 orally twice daily for the first 14 days of a 21-day cycle (N=995) or leucovorin 20 mg/m^2 intravenously followed by fluorouracil 425 mg/m^2 as an intravenous bolus on days 1 to 5 of each 28-day cycle (N=974). Among patients who received XELODA, the median duration of treatment was 5.4 months.

Deaths due to all causes occurred in 0.8% of patients who received XELODA on study or within 28 days of receiving study drug. Permanent discontinuation due to an adverse reaction occurred in 11% of patients who received XELODA.

Most common adverse reactions (>30%) were palmar-plantar erythrodysesthesia syndrome, diarrhea, and nausea.

Tables 2 and 3 summarize the adverse reactions and laboratory abnormalities in X-ACT.

Table 2 Adverse Reactions (≥10%) in Patients Who Received XELODA for Adjuvant Treatment of Colon Cancer in X-ACT
Adverse Reaction | XELODA (N=995) |  | Fluorouracil + Leucovorin (N=974)
 | All Grades (%) | Grade 3 or 4 (%) | All Grades (%) | Grade 3 or 4 (%)
Skin and Subcutaneous Tissue
Palmar-plantar erythrodysesthesia syndrome | 60 | 17 | 9 | <1
Gastrointestinal
Diarrhea | 47 | 12 | 65 | 14
Nausea | 34 | 2 | 47 | 2
Stomatitis | 22 | 2 | 60 | 14
Vomiting | 15 | 2 | 21 | 2
Abdominal pain | 14 | 3 | 16 | 2
General
Fatigue | 16 | <1 | 16 | 1
Asthenia | 10 | <1 | 10 | 1
Lethargy | 10 | <1 | 9 | <1

Clinically relevant adverse reactions in <10% of patients are presented below:

Eye: conjunctivitis

Gastrointestinal: constipation, upper abdominal pain, dyspepsia

General: pyrexia

Metabolism and Nutrition: anorexia

Nervous System: dizziness, dysgeusia, headache

Skin & Subcutaneous Tissue: rash, alopecia, erythema

Table 3 Grade 3 or 4 Laboratory Abnormalities (>1%) in Patients Who Received XELODA as a Single Agent for Adjuvant Treatment of Colon Cancer in X-ACT
Laboratory Abnormality | XELODA (N=995) | Fluorouracil + Leucovorin (N=974)
Laboratory Abnormality | Grade 3 or 4 | Grade 3 or 4
Laboratory Abnormality | (%) | (%)
Bilirubin increased | 20 | 6
Lymphocytes decreased | 13 | 13
Neutrophils/granulocytes decreased | 2.4 | 26
Calcium decreased | 2.3 | 2.2
Neutrophils decreased | 2.2 | 26
ALT increased | 1.6 | 0.6
Calcium increased | 1.1 | 0.7
Hemoglobin decreased | 1 | 1.2
Platelets decreased | 1 | 0.7

In Combination with Oxaliplatin-Containing Regimens

The safety of XELODA for the perioperative treatment of adults with Stage III colon cancer as a component of a combination chemotherapy regimen was derived from published literature [see Clinical Studies (14.1)]. The safety of XELODA for the adjuvant treatment of patients with Stage III colon cancer as a component of a combination chemotherapy regimen was similar to those in patients treated with XELODA as a single agent, with the exception of an increased incidence of neurosensory toxicity.

Perioperative Treatment of Rectal Cancer

The safety of XELODA for the perioperative treatment of adults with locally advanced rectal cancer as a component of chemoradiotherapy was derived from published literature [see Clinical Studies (14.1)]. The safety of XELODA for the perioperative treatment of adults with locally advanced rectal cancer as a component of chemoradiotherapy was similar to those in patients treated with XELODA as a single agent, with the exception of an increased incidence of diarrhea.

Metastatic Colorectal Cancer

Single Agent

The safety of XELODA as a single agent was evaluated in a pooled metastatic colorectal cancer population (Study SO14695 and Study SO14796) [see Clinical Studies (14.1)]. Patients received XELODA 1,250 mg/m^2 orally twice a day for the first 14 days of a 21-day cycle (N=596) or leucovorin 20 mg/m^2 intravenously followed by fluorouracil 425 mg/m^2 as an intravenous bolus on days 1 to 5 of each 28-day cycle (N=593). Among the patients who received XELODA, the median duration of treatment was 4.6 months.

Deaths due to all causes occurred in 8% of patients who received XELODA on study or within 28 days of receiving study drug. Permanent discontinuation due to an adverse reaction or intercurrent illness occurred in 13% of patients who received XELODA.

Most common adverse reactions (>30%) were anemia, diarrhea, palmar-plantar erythrodysesthesia syndrome, hyperbilirubinemia, nausea, fatigue, and abdominal pain.

Table 4 shows the adverse reactions occurring in this pooled colorectal cancer population.

Table 4 Adverse Reactions (≥10%) in Patients Who Received XELODA in Pooled Metastatic Colorectal Cancer Population (Study SO14695 and Study SO14796)
Adverse Reaction | XELODA |  |  | Fluorouracil + Leucovorin
Adverse Reaction | (N=596) |  |  | (N=593)
Adverse Reaction | All Grades (%) | Grade 3 (%) | Grade 4 (%) | All Grades (%) | Grade 3 (%) | Grade 4 (%)
Blood and Lymphatic System
Anemia | 80 | 2 | <1 | 79 | 1 | <1
Neutropenia | 13 | 1 | 2 | 46 | 8 | 13
Gastrointestinal
Diarrhea | 55 | 13 | 2 | 61 | 10 | 2
Nausea | 43 | 4 | – | 51 | 3 | <1
Abdominal pain | 35 | 9 | <1 | 31 | 5 | –
Vomiting | 27 | 4 | <1 | 30 | 4 | <1
Stomatitis | 25 | 2 | <1 | 62 | 14 | 1
Constipation | 14 | 1 | <1 | 17 | 1 | –
Gastrointestinal motility disorder | 10 | <1 | – | 7 | <1 | –
Oral discomfort | 10 | – | – | 10 | – | –
Skin and Subcutaneous Tissue
Palmar-plantar erythrodysesthesia syndrome | 54 | 17 | NA | 6 | 1 | NA
Dermatitis | 27 | 1 | – | 26 | 1 | –
Hepatobiliary
Hyperbilirubinemia | 48 | 18 | 5 | 17 | 3 | 3
General
Fatigue [Includes weakness] | 42 | 4 | – | 46 | 4 | –
Pyrexia | 18 | 1 | – | 21 | 2 | –
Edema | 15 | 1 | – | 9 | 1 | –
Pain | 12 | 1 | – | 10 | 1 | –
Metabolism and Nutrition
Decreased appetite | 26 | 3 | <1 | 31 | 2 | <1
Respiratory Thoracic and Mediastinal
Dyspnea | 14 | 1 | – | 10 | <1 | 1
Eye
Eye irritation | 13 | – | – | 10 | <1 | –
Nervous System
Peripheral sensory neuropathy | 10 | – | – | 4 | – | –
Headache | 10 | 1 | – | 7 | – | –
Musculoskeletal
Back pain | 10 | 2 | – | 9 | <1 | –
– Not observed
NA = Not Applicable

Clinically relevant adverse reactions in <10% of patients are presented below:

Eye: abnormal vision

Gastrointestinal: upper gastrointestinal tract inflammatory disorders, gastrointestinal hemorrhage, ileus

General: chest pain

Infections: viral

Metabolism and Nutrition: dehydration

Musculoskeletal: arthralgia

Nervous System: dizziness (excluding vertigo), insomnia, taste disturbance

Psychiatric: mood alteration, depression

Respiratory, Thoracic, and Mediastinal: cough, pharyngeal disorder

Skin and Subcutaneous Tissue: skin discoloration, alopecia

Vascular: venous thrombosis

In Combination with Oxaliplatin

The safety of XELODA for the treatment of patients with unresectable or metastatic colorectal cancer as a component of a combination chemotherapy regimen was derived from published literature [see Clinical Studies (14.1)]. The safety of XELODA for the treatment of patients with unresectable or metastatic colorectal cancer as a component of a combination chemotherapy regimen was similar to those in patients treated with XELODA as a single agent, with the exception of an increased incidence of peripheral neuropathy.

Metastatic Breast Cancer

In Combination with Docetaxel

The safety of XELODA in combination with docetaxel was evaluated in patients with metastatic breast cancer in Study SO14999 [see Clinical Studies (14.2)]. Patients received XELODA 1,250 mg/m^2 orally twice daily for the first 14 days of a 21-day cycle with docetaxel 75 mg/m^2 as 1-hour intravenous infusion on day 1 of each 21-day cycle for at least 6 weeks or docetaxel 100 mg/m^2 as a 1-hour intravenous infusion on day 1 of each 21-day cycle for at least 6 weeks. Among patients who received XELODA, the mean duration of treatment was 4.2 months.

Permanent discontinuation due to an adverse reaction occurred in 26% of patients who received XELODA. Dosage interruptions due to an adverse reaction occurred in 79% of patients who received XELODA and dosage reductions due to an adverse reaction occurred in 65%.

Most common adverse reactions (>30%) were diarrhea, stomatitis, palmar-plantar erythrodysesthesia syndrome, nausea, alopecia, vomiting, edema, and abdominal pain.

Table 5 summarizes the adverse reactions in Study SO14999.

Table 5 Adverse Reactions (≥10%) in Patients Who Received XELODA with Docetaxel for Metastatic Breast Cancer in Study SO14999
Adverse Reaction | XELODA with Docetaxel |  |  | Docetaxel
Adverse Reaction | (N=251) |  |  | (N=255)
Adverse Reaction | All Grades (%) | Grade 3 (%) | Grade 4 (%) | All Grades (%) | Grade 3 (%) | Grade 4 (%)
Gastrointestinal
Diarrhea | 67 | 14 | <1 | 48 | 5 | <1
Stomatitis | 67 | 17 | <1 | 43 | 5 | –
Nausea | 45 | 7 | – | 36 | 2 | –
Vomiting | 35 | 4 | 1 | 24 | 2 | –
Abdominal pain | 30 | 3 | <1 | 24 | 2 | –
Constipation | 20 | 2 | – | 18 | – | –
Dyspepsia | 14 | – | – | 8 | 1 | –
Skin and Subcutaneous Tissue
Palmar-plantar erythrodysesthesia syndrome | 63 | 24 | NA | 8 | 1 | NA
Alopecia | 41 | 6 | – | 42 | 7 | –
Nail disorder | 14 | 2 | – | 15 | – | –
Cardiac
Edema | 33 | <2 | – | 34 | <3 | 1
General
Pyrexia | 28 | 2 | – | 34 | 2 | –
Asthenia | 26 | 4 | <1 | 25 | 6 | –
Fatigue | 22 | 4 | – | 27 | 6 | –
Weakness | 16 | 2 | – | 11 | 2 | –
Pain in Limb | 13 | <1 | – | 13 | 2 | –
Blood and Lymphatic System
Neutropenic fever | 16 | 3 | 13 | 21 | 5 | 16
Nervous System
Taste disturbance | 16 | <1 | – | 14 | <1 | –
Headache | 15 | 3 | – | 15 | 2 | –
Paresthesia | 12 | <1 | – | 16 | 1 | –
Dizziness | 12 | – | – | 8 | <1 | –
Musculoskeletal and Connective Tissue
Arthralgia | 15 | 2 | – | 24 | 3 | –
Myalgia | 15 | 2 | – | 25 | 2 | –
Back Pain | 12 | <1 | – | 11 | 3 | –
Respiratory, Thoracic and Mediastinal
Dyspnea | 14 | 2 | <1 | 16 | 2 | –
Cough | 13 | 1 | – | 22 | <1 | –
Sore Throat | 12 | 2 | – | 11 | <1 | –
Metabolism and Nutrition
Anorexia | 13 | <1 | – | 11 | <1 | –
Appetite decreased | 10 | – | – | 5 | – | –
Dehydration | 10 | 2 | – | 7 | <1 | <1
Eye
Lacrimation increased | 12 | – | – | 7 | <1 | –
– Not observed
NA = Not Applicable

Clinically relevant adverse reactions in <10% of patients are presented below:

Blood and Lymphatic System: agranulocytosis, prothrombin decreased

Cardiac: supraventricular tachycardia

Eye: conjunctivitis, eye irritation

Gastrointestinal: ileus, necrotizing enterocolitis, esophageal ulcer, hemorrhagic diarrhea, dry mouth

General: chest pain (non-cardiac), lethargy, pain, influenza-like illness

Hepatobiliary: jaundice, abnormal liver function tests, hepatic failure, hepatic coma, hepatotoxicity

Immune System: hypersensitivity

Infection: hypoesthesia, neutropenic sepsis, sepsis, bronchopneumonia, oral candidiasis, urinary tract infection

Metabolism and Nutrition: weight decreased

Musculoskeletal and Connective Tissue: bone pain

Nervous System: insomnia, peripheral neuropathy, ataxia, syncope, taste loss, polyneuropathy, migraine

Psychiatric: depression

Renal and Urinary: renal failure

Respiratory, Thoracic and Mediastinal: upper respiratory tract infection, pleural effusion, epistaxis, rhinorrhea

Skin and Subcutaneous Tissue: pruritis, rash erythematous, dermatitis, nail discoloration, onycholysis

Vascular: lymphedema, hypotension, venous phlebitis and thrombophlebitis, postural hypotension, flushing

Table 6 summarizes the laboratory abnormalities in this trial.

Table 6 Laboratory Abnormalities (≥20%) in Patients Who Received XELODA with Docetaxel for Metastatic Breast Cancer in Study SO14999
Laboratory Abnormality | XELODA with Docetaxel |  |  | Docetaxel
Laboratory Abnormality | (N=251) |  |  | (N=255)
Laboratory Abnormality | All Grades (%) | Grade 3 (%) | Grade 4 (%) | All Grades (%) | Grade 3 (%) | Grade 4 (%)
Hematologic
Lymphocytopenia | 99 | 48 | 41 | 98 | 44 | 40
Leukopenia | 91 | 37 | 24 | 88 | 42 | 33
Neutropenia | 86 | 20 | 49 | 87 | 10 | 66
Anemia | 80 | 7 | 3 | 83 | 5 | <1
Thrombocytopenia | 41 | 2 | 1 | 23 | 1 | 2
Hepatobiliary
Hyperbilirubinemia | 20 | 7 | 2 | 6 | 2 | 2

Single Agent

The safety of XELODA as a single agent was evaluated in patients with metastatic breast cancer in Study SO14697 [see Clinical Studies (14.2)]. Patients received XELODA 1,250 mg/m^2 orally twice daily for the first 14 days of a 21-day cycle. The mean duration of treatment was 3.7 months.

Permanent discontinuation due to an adverse reaction or intercurrent illness occurred in 8% of patients.

Most common adverse reactions (>30%) were lymphopenia, anemia, diarrhea, hand-and-foot syndrome, nausea, fatigue, vomiting, and dermatitis.

Table 7 summarizes the adverse reactions in Study SO14697.

Table 7 Adverse Reactions (≥10%) in Patients Who Received XELODA for Metastatic Breast Cancer in Study SO14697
Adverse Reaction | XELODA (n=162)
Adverse Reaction | All Grades (%) | Grade 3 (%) | Grade 4 (%)
Adverse Reaction | Blood and Lymphatic System
Lymphopenia | 94 | 44 | 15
Anemia | 72 | 3 | 1
Neutropenia | 26 | 2 | 2
Thrombocytopenia | 24 | 3 | 1
Gastrointestinal
Diarrhea | 57 | 12 | 3
Nausea | 53 | 4 | –
Vomiting | 37 | 4 | –
Stomatitis | 24 | 7 | –
Abdominal pain | 20 | 4 | –
Constipation | 15 | 1 | –
Skin and Subcutaneous Tissue
Hand-and-foot syndrome | 57 | 11 | NA
Dermatitis | 37 | 1 | –
General
Fatigue | 41 | 8 | –
Pyrexia | 12 | 1 | –
Metabolism and Nutrition
Anorexia | 23 | 3 | –
Hepatobiliary
Hyperbilirubinemia | 22 | 9 | 2
Nervous System
Paresthesia | 21 | 1 | –
Eye
Eye irritation | 15 | – | –
– = Not observed
NA = Not Applicable

Pooled Safety Population

Clinically relevant adverse reactions in <10% of patients who received XELODA as a single agent are presented below.

Blood & Lymphatic System: leukopenia, coagulation disorder, bone marrow depression, pancytopenia

Cardiac: tachycardia, bradycardia, atrial fibrillation, myocarditis, edema

Ear: vertigo

Eye: conjunctivitis

Gastrointestinal: abdominal distension, dysphagia, proctalgia, gastric ulcer, ileus, gastroenteritis, dyspepsia

General: chest pain, influenza-like illness, hot flushes, pain, thirst, fibrosis, hemorrhage, edema, pain in limb

Hepatobiliary: hepatic fibrosis, hepatitis, cholestatic hepatitis, abnormal liver function tests

Immune System: drug hypersensitivity

Infections: bronchitis, pneumonia, keratoconjunctivitis, sepsis, fungal infections

Metabolism and Nutrition: cachexia, hypertriglyceridemia, hypokalemia, hypomagnesemia, dehydration

Musculoskeletal and Connective Tissue: myalgia, arthritis, muscle weakness

Nervous System: insomnia, ataxia, tremor, dysphasia, encephalopathy, dysarthria, impaired balance, headache, dizziness

Psychiatric: depression, confusion

Renal and Urinary: renal impairment

Respiratory, Mediastinal and Thoracic: cough, epistaxis, respiratory distress, dyspnea

Skin and Subcutaneous Tissue: nail disorder, sweating increased, photosensitivity reaction, skin ulceration, pruritus, radiation recall syndrome

Vascular: hypotension, hypertension, lymphedema, pulmonary embolism

Unresectable or Metastatic Gastric, Esophageal, or Gastroesophageal Junction Cancer

The safety of XELODA for the treatment of adults with unresectable or metastatic gastric, esophageal, or gastroesophageal junction cancer as a component of a combination chemotherapy regimen was derived from published literature [see Clinical Studies (14.3)]. The safety of XELODA for the treatment of adults with unresectable or metastatic gastric, esophageal, or gastroesophageal junction cancer as a component of a combination chemotherapy regimen was consistent with the known safety profile of XELODA.

The safety of XELODA for the treatment of patients with HER2-overexpressing metastatic gastric or gastroesophageal junction adenocarcinoma who have not received prior treatment for metastatic disease as a component of a combination regimen was derived from the published literature [see Clinical Studies (14.3)]. The safety of XELODA for the treatment of patients with HER2-overexpressing metastatic gastric or gastroesophageal junction adenocarcinoma was consistent with the known safety profile of XELODA.

Pancreatic Cancer

The safety of XELODA for the adjuvant treatment of adults with pancreatic adenocarcinoma as a component of a combination chemotherapy regimen was derived from the published literature [see Clinical Studies (14.4)]. The safety of XELODA for the adjuvant treatment of adults with pancreatic adenocarcinoma as a component of a combination chemotherapy regimen was consistent with the known safety profile of XELODA.

6.2 Postmarketing Experience

The following adverse reactions have been identified during post-approval use of XELODA. Because these reactions are reported voluntarily from a population of uncertain size, it is not always possible to reliably estimate their frequency or establish a causal relationship to drug exposure.

Eye: lacrimal duct stenosis, corneal disorders including keratitis

Hepatobiliary: hepatic failure

Immune System Disorders: angioedema

Nervous System: toxic leukoencephalopathy

Renal & Urinary: acute renal failure secondary to dehydration including fatal outcome

Skin & Subcutaneous Tissue: cutaneous lupus erythematosus, severe skin reactions such as Stevens-Johnson Syndrome and Toxic Epidermal Necrolysis (TEN), persistent or severe PPES can eventually lead to loss of fingerprints

7 DRUG INTERACTIONS

7.1 Effect of Other Drugs on XELODA

Allopurinol

Concomitant use with allopurinol may decrease concentration of capecitabine's active metabolites [see Clinical Pharmacology (12.3)], which may decrease efficacy. Avoid concomitant use of allopurinol with XELODA.

Leucovorin

The concentration of fluorouracil is increased and its toxicity may be enhanced by leucovorin, folic acid, or folate analog products. Deaths from severe enterocolitis, diarrhea, and dehydration have been reported in elderly patients receiving weekly leucovorin and fluorouracil.

Instruct patients not to take products containing folic acid or folate analog products unless directed to do so by their healthcare provider.

7.2 Effect of Xeloda on Other Drugs

CYP2C9 Substrates

XELODA increased exposure of CYP2C9 substrates [see Clinical Pharmacology (12.3)], which may increase the risk of adverse reactions related to these substrates. Closely monitor for adverse reactions of CYP2C9 substrates where minimal concentration changes may lead to serious adverse reactions when used concomitantly with XELODA (e.g., anticoagulants, antidiabetic drugs).

Vitamin K Antagonists

XELODA increases exposure of vitamin K antagonist [see Clinical Pharmacology (12.3)], which may alter coagulation parameters and/or bleeding and could result in death [see Warning and Precautions (5.1)]. These events may occur within days of treatment initiation and up to 1 month after discontinuation of XELODA.

Monitor INR more frequently and refer to the prescribing information of oral vitamin K antagonist for dosage adjustment, as appropriate, when XELODA is used concomitantly with vitamin K antagonist.

Phenytoin

XELODA may increases exposure of phenytoin, which may increase the risk of adverse reactions related to phenytoin. Closely monitor phenytoin levels and refer to the prescribing information of phenytoin for dosage adjustment, as appropriate, when XELODA is used concomitantly with phenytoin.

7.3 Nephrotoxic Drugs

Due of the additive pharmacologic effect, concomitant use of XELODA with other drugs known to cause renal toxicity may increase the risk of renal toxicity [see Warnings and Precautions (5.6)]. Closely monitor for signs of renal toxicity when XELODA is used concomitantly with nephrotoxic drugs (e.g. platinum salts, irinotecan, methotrexate, intravenous bisphosphonates).

8 USE IN SPECIFIC POPULATIONS

8.1 Pregnancy

Risk Summary

Based on findings in animal reproduction studies and its mechanism of action [see Clinical Pharmacology (12.1)], XELODA can cause fetal harm when administered to a pregnant woman. Available human data with XELODA use in pregnant women is not sufficient to inform the drug-associated risk. In animal reproduction studies, administration of capecitabine to pregnant animals during the period of organogenesis caused embryolethality and teratogenicity in mice and embryolethality in monkeys at 0.2 and 0.6 times the exposure (AUC) in patients receiving the recommended dose of 1,250 mg/m^2 twice daily, respectively (see Data). Advise pregnant women of the potential risk to a fetus.

The estimated background risk of major birth defects and miscarriage for the indicated population is unknown. All pregnancies have a background risk of birth defect, loss, or other adverse outcomes. In the U.S. general population, the estimated background risk of major birth defects and miscarriage in clinically recognized pregnancies is 2% to 4% and 15% to 20%, respectively.

Data

Animal Data

Oral administration of capecitabine to pregnant mice during the period of organogenesis at a dose of 198 mg/kg/day caused malformations and embryo lethality. In separate pharmacokinetic studies, this dose in mice produced 5'-DFUR AUC values that were approximately 0.2 times the AUC values in patients administered the recommended daily dose. Malformations in mice included cleft palate, anophthalmia, microphthalmia, oligodactyly, polydactyly, syndactyly, kinky tail and dilation of cerebral ventricles. Oral administration of capecitabine to pregnant monkeys during the period of organogenesis at a dose of 90 mg/kg/day, caused fetal lethality. This dose produced 5'-DFUR AUC values that were approximately 0.6 times the AUC values in patients administered the recommended daily dose.

8.2 Lactation

Risk Summary

There is no information regarding the presence of capecitabine or its metabolites in human milk, or on its effects on milk production or the breastfed child. Capecitabine metabolites were present in the milk of lactating mice (see Data). Because of the potential for serious adverse reactions in a breastfed child, advise women not to breastfeed during treatment with XELODA and for 1 week after the last dose.

Data

Lactating mice given a single oral dose of capecitabine excreted significant amounts of capecitabine metabolites into the milk.

8.3 Females and Males of Reproductive Potential

XELODA can cause fetal harm when administered to a pregnant woman [see Use in Specific Populations (8.1)].

Pregnancy Testing

Verify pregnancy status in females of reproductive potential prior to initiating XELODA.

Contraception

Females

Advise females of reproductive potential to use effective contraception during treatment with XELODA and for 6 months after the last dose.

Males

Based on genotoxicity findings, advise males with female partners of reproductive potential to use effective contraception during treatment with XELODA and for 3 months after the last dose [see Nonclinical Toxicology (13.1)].

Infertility

Based on animal studies, XELODA may impair fertility in females and males of reproductive potential [see Nonclinical Toxicology (13.1)].

8.4 Pediatric Use

The safety and effectiveness of XELODA in pediatric patients have not been established.

Safety and effectiveness were assessed, but not established in two single arm studies in 56 pediatric patients aged 3 months to <17 years with newly diagnosed gliomas. In both trials, pediatric patients received an investigational pediatric formulation of capecitabine concomitantly with and following completion of radiation therapy (total dose of 5580 cGy in 180 cGy fractions). The relative bioavailability of the investigational formulation to XELODA was similar.

The adverse reaction profile was consistent with that of adults, with the exception of laboratory abnormalities which occurred more commonly in pediatric patients. The most frequently reported laboratory abnormalities (per-patient incidence ≥ 40%) were increased ALT (75%), lymphocytopenia (73%), hypokalemia (68%), thrombocytopenia (57%), hypoalbuminemia (55%), neutropenia (50%), low hematocrit (50%), hypocalcemia (48%), hypophosphatemia (45%) and hyponatremia (45%).

8.5 Geriatric Use

Of 7938 patients with colorectal cancer who were treated with XELODA, 33% were older than 65 years. Of the 4536 patients with metastatic breast cancer who were treated with XELODA, 18% were older than 65 years.

Of 1951 patients with gastric, esophageal, or gastrointestinal junction cancer who were treated with XELODA, 26% were older than 65 years.

Of 364 patients with pancreatic cancer who received adjuvant treatment with XELODA, 47% were 65 years or older.

No overall differences in efficacy were observed comparing older versus younger patients with colorectal cancer, gastric, esophageal or gastrointestinal junction cancer, or pancreatic cancer using the approved recommended dosages and treatment regimens.

Older patients experience increased gastrointestinal toxicity due to XELODA compared to younger patients. Deaths from severe enterocolitis, diarrhea, and dehydration have been reported in elderly patients receiving weekly leucovorin and fluorouracil [see Drug Interactions (7.1)].

8.6 Renal Impairment

The exposure of capecitabine and its inactive metabolites (5-DFUR and FBAL) increases in patients with CLcr <50 mL/min as determined by Cockcroft-Gault [see Clinical Pharmacology (12.3)]. Reduce the dosage for patients with CLcr of 30 to 50 mL/min [see Dosage and Administration (2.6)]. There is limited experience with XELODA in patients with CLcr <30 mL/min, and a dosage has not been established in those patients. If no treatment alternative exists, XELODA could be administered to such patients on an individual basis applying a reduced starting dose, close monitoring of a patient's clinical and biochemical data and dose modifications guided by observed adverse reactions.

8.7 Hepatic Impairment

The exposure of capecitabine increases in patients with mild to moderate hepatic impairment. The effect of severe hepatic impairment on the safety and pharmacokinetics of XELODA is unknown [see Clinical Pharmacology (12.3)]. Monitor patients with hepatic impairment more frequently for adverse reactions.

10 OVERDOSAGE

Administer uridine triacetate within 96 hours for management of XELODA overdose.

Although no clinical experience using dialysis as a treatment for XELODA overdose has been reported, dialysis may be of benefit in reducing circulating concentrations of 5'-DFUR, a low–molecular-weight metabolite of the parent compound.

11 DESCRIPTION

Capecitabine is a nucleoside metabolic inhibitor. The chemical name is 5'-deoxy-5-fluoro-N-[(pentyloxy) carbonyl]-cytidine and has a molecular formula of C15H22FN3O6 and a molecular weight of 359.35. Capecitabine has the following structural formula:

Capecitabine is a white to off-white crystalline powder with an aqueous solubility of 26 mg/mL at 20°C.

XELODA (capecitabine) is supplied as biconvex, oblong film-coated tablets for oral use. Each light peach-colored tablet contains 150 mg capecitabine and each peach-colored tablet contains 500 mg capecitabine. The inactive ingredients in XELODA include: anhydrous lactose, croscarmellose sodium, hydroxypropyl methylcellulose, microcrystalline cellulose, magnesium stearate and purified water. The peach or light peach film coating contains hydroxypropyl methylcellulose, talc, titanium dioxide, and synthetic yellow and red iron oxides.

12 CLINICAL PHARMACOLOGY

12.1 Mechanism of Action

Capecitabine is metabolized to fluorouracil in vivo. Both normal and tumor cells metabolize fluorouracil to 5-fluoro-2'-deoxyuridine monophosphate (FdUMP) and 5-fluorouridine triphosphate (FUTP). These metabolites cause cell injury by two different mechanisms. First, FdUMP and the folate cofactor, N^5-10-methylenetetrahydrofolate, bind to thymidylate synthase (TS) to form a covalently bound ternary complex. This binding inhibits the formation of thymidylate from 2'-deoxyuridylate. Thymidylate is the necessary precursor of thymidine triphosphate, which is essential for the synthesis of DNA, so that a deficiency of this compound can inhibit cell division. Second, nuclear transcriptional enzymes can mistakenly incorporate FUTP in place of uridine triphosphate (UTP) during the synthesis of RNA. This metabolic error can interfere with RNA processing and protein synthesis.

12.2 Pharmacodynamics

Population-based exposure-effect analyses demonstrated a positive association between AUC of fluorouracil and grade 3-4 hyperbilirubinemia.

12.3 Pharmacokinetics

The AUC of capecitabine and its metabolite 5'-DFCR increases proportionally over a dosage range of 500 mg/m^2/day to 3,500 mg/m^2/day (0.2 to 1.4 times the approved recommended dosage). The AUC of capecitabine's metabolites 5'-DFUR and fluorouracil increased greater than proportional to the dose. The interpatient variability in the Cmax and AUC of fluorouracil was greater than 85%.

Absorption

Following oral administration of XELODA 1,255 mg/m^2 orally twice daily (the recommended dosage when used as single agent), the median Tmax of capecitabine and its metabolite fluorouracil was approximately 1.5 hours and 2 hours, respectively.

Effect of Food

Following administration of a meal (breakfast medium-rich in fat and carbohydrates), the mean Cmax and AUC0-INF of capecitabine was decreased by 60% and 34%, respectively. The mean Cmax and AUC0-INF of fluorouracil were also decreased by 37 % and 12%, respectively. The Tmax of both capecitabine and fluorouracil was delayed by 1.5 hours.

Distribution

Plasma protein binding of capecitabine and its metabolites is less than 60% and is not concentration-dependent. Capecitabine was primarily bound to human albumin (approximately 35%).

Following oral administration of XELODA 7 days before surgery in patients with colorectal cancer, the median ratio of concentration for the active metabolite fluorouracil in colorectal tumors to adjacent tissues was 2.9 (range: 0.9 to 8.0).

Elimination

The elimination half-lives of capecitabine and fluorouracil were approximately 0.75 hour.

Metabolism

Capecitabine undergoes metabolism by carboxylesterase and is hydrolyzed to 5'-DFCR. 5'-DFCR is subsequently converted to 5'-DFUR by cytidine deaminase. 5'-DFUR is then hydrolized by thymidine phosphorylase (dThdPase) enzymes to the active metabolite fluorouracil.

Fluorouracil is subsequently metabolized by dihydropyrimidine dehydrogenase to 5-fluoro-5, 6-dihydro-fluorouracil (FUH2). The pyrimidine ring of FUH2 is cleaved by dihydropyrimidinase to yield 5-fluoro-ureido-propionic acid (FUPA). Finally, FUPA is cleaved by β-ureido-propionase to α-fluoro-β-alanine (FBAL).

Excretion

Following administration of radiolabeled capecitabine, 96% of the administered capecitabine dose was recovered in urine (3% unchanged and 57% as metabolite FBAL) and 2.6% in feces.

Specific Populations

Following therapeutic doses of XELODA, no clinically meaningful difference in the pharmacokinetics of 5'-DFUR, fluorouracil or FBAL were observed based on sex (202 females and 303 males) and race (455 White, 22 Black, and 28 Other). No clinically meaningful difference on the pharmacokinetics of 5'-DFUR and fluorouracil were observed based on age (range: 27 to 86 years); however, the AUC of FBAL increased by 15% following a 20% increase in age.

Racial or Ethnic Groups

Following administration of XELODA 825 mg/m^2 orally twice daily for 14 days (0.66 times the recommended dosage), the Cmax and AUC of capecitabine decreased by 36% and 24%, respectively in Japanese patients (n=18) compared to White patients (n=22). The Cmax and AUC of FBAL decreased by approximately 25% and 34%, respectively in Japanese patients compared to White patients; however, the clinical significance of these differences is unknown. No clinically significant differences in the pharmacokinetics of 5'-DFCR, 5'-DFUR or fluorouracil were observed.

Patients with Renal Impairment

Table 8 Effect of Renal Impairment on the Pharmacokinetics of Capecitabine, 5'-DFUR, and FBAL
Renal Impairment* | Changes in AUC†
Renal Impairment* | Capecitabine | 5'-DFUR‡ | FBAL‡ | 5-FU
CLcr= Creatine Clearance, AUC= Area under the plasma concentration-time curve
CLcr 30 to 50 mL/min | Increased by 25% | Increased by 42% | Increased by 85% | No relevant change
CLcr <30 mL/min | Increased by 25% | Increased by 71% | Increased by 258% | Increased by 24%
* Compared to patients with CLcr >80 mL/min
† Following administration of XELODA 1,250 mg/m2 orally twice daily; day 1 observations
‡ Capecitabine metabolite

Patients with Hepatic Impairment

AUC0-INF and Cmax of capecitabine's active principle, fluorouracil, were not affected in patients with mild or moderate hepatic impairment compared to patients with normal hepatic function. The AUC0-INF and Cmax of capecitabine increased by 60%. The effect of severe hepatic impairment on the pharmacokinetics of capecitabine and its metabolites are unknown.

Drug Interaction Studies

Clinical Studies

Effect of Capecitabine on Warfarin: In four patients with cancer, chronic administration of XELODA 1,250 mg/m^2 twice daily with a single dose of warfarin 20 mg increased the mean AUC of S-warfarin by 57% and decreased its clearance by 37%. Baseline corrected AUC of INR in these 4 patients increased by 2.8-fold, and the maximum observed mean INR value was increased by 91%.

Effect of Capecitabine on Celecoxib: Concomitant administration of multiple doses of capecitabine (XELODA 1,000 mg/m^2 twice daily for 14 days) increased celecoxib (sensitive CYP2C9 substrate) AUC by 28%, Cmax by 24% and Ctrough by 30%.

Effect of Antacids on Capecitabine: When an aluminum hydroxide- and magnesium hydroxide-containing antacid was administered immediately after a XELODA dose of 1,250 mg/m^2 in patients with cancer, AUC and Cmax increased by 16% and 35%, respectively, for capecitabine and by 18% and 22%, respectively, for 5'-DFCR. No effect was observed on the other three major metabolites (5'-DFUR, fluorouracil, FBAL) of XELODA.

Effect of Allopurinol on Capecitabine: Concomitant use with allopurinol may decrease conversion of capecitabine to the active metabolites, FdUMP and FUTP.

Effect of Capecitabine on Docetaxel and Effect of Docetaxel on Capecitabine: XELODA had no effect on the pharmacokinetics of docetaxel (Cmax and AUC) and docetaxel has no effect on the pharmacokinetics of capecitabine and the fluorouracil precursor 5'-DFUR.

In Vitro Studies

Cytochrome P450 (CYP) Enzymes: Capecitabine and its metabolites (5'-DFUR, 5'-DFCR, fluorouracil, and FBAL) did not inhibit CYP1A2, CYP2A6, CYP3A4, CYP2C19, CYP2D6, or CYP2E1 in vitro.

12.5 Pharmacogenomics

The DPYD gene encodes the enzyme DPD, which is responsible for the catabolism of >80% of fluorouracil. Approximately 3-5% of White populations have partial DPD deficiency and 0.2% of White populations have complete DPD deficiency, which may be due to certain genetic no function or decreased function variants in DPYD resulting in partial to complete or near complete absence of enzyme activity. DPD deficiency is estimated to be more prevalent in Black or African American populations compared to White populations. Insufficient information is available to estimate the prevalence of DPD deficiency in other populations.

Patients who are homozygous or compound heterozygous for no function DPYD variants (i.e., carry two DPYD variants that results in no DPD enzyme activity) or are compound heterozygous for a no function DPYD variant plus a decreased function DPYD variant have complete DPD deficiency and are at increased risk for acute early-onset of toxicity and serious life-threatening, or fatal adverse reactions with XELODA. Partial DPD deficiency can result from the presence of either two decreased function DPYD variants or one normal function plus either a decreased function or a no function DPYD variant. Patients with partial DPD deficiency may also be at an increased risk for toxicity from XELODA.

Several DPYD variants observed with variable frequency across populations have been associated with reduced or no DPD activity, especially when present as homozygous or compound heterozygous variants.These include c.1905+1G>A (DPYD *2A), c.1679T>G (DPYD *13), c.2846A>T, c.1129-5923C>G (Haplotype B3), and c557A>G. DPYD*2A and DPYD*13 are no function variants, and c.2846A>T, c.1129-5923C>G, and c557A>G are decreased function variants. This is not a complete listing of all DPYD variants that may result in DPD deficiency [see Warnings and Precautions (5.1)].

13 NONCLINICAL TOXICOLOGY

13.1 Carcinogenesis, Mutagenesis, Impairment of Fertility

Adequate studies investigating the carcinogenic potential of capecitabine have not been conducted. Capecitabine was not mutagenic in vitro to bacteria (Ames test) or mammalian cells (Chinese hamster V79/HPRT gene mutation assay). Capecitabine was clastogenic in vitro to human peripheral blood lymphocytes but not clastogenic in vivo to mouse bone marrow (micronucleus test). Fluorouracil causes mutations in bacteria and yeast. Fluorouracil also causes chromosomal abnormalities in the mouse micronucleus test in vivo.

In studies of fertility and general reproductive performance in female mice, oral capecitabine doses of 760 mg/kg/day (about 2,300 mg/m^2/day) disturbed estrus and consequently caused a decrease in fertility. In mice that became pregnant, no fetuses survived this dose. The disturbance in estrus was reversible. In males, this dose caused degenerative changes in the testes, including decreases in the number of spermatocytes and spermatids. In separate pharmacokinetic studies, this dose in mice produced 5'-DFUR AUC values about 0.7 times the corresponding values in patients administered the recommended daily dose.

14 CLINICAL STUDIES

14.1 Colorectal Cancer

Adjuvant Treatment of Colon Cancer

Single Agent

The efficacy of XELODA was evaluated in X-ACT (NCT00009737), a multicenter, randomized, controlled clinical trial. Eligible patients were between 18 and 75 years of age with histologically-confirmed Dukes' Stage C colon cancer with at least one positive lymph node and to have undergone (within 8 weeks prior to randomization) complete resection of the primary tumor without macroscopic or microscopic evidence of remaining tumor. Patients were also required to have no prior cytotoxic chemotherapy or immunotherapy (except steroids) and have an ECOG performance status of 0 or 1 (KPS ≥70%), ANC≥1.5×10^9/L, platelets ≥100×10^9/L, serum creatinine ≤1.5 ULN, total bilirubin ≤1.5 ULN, AST/ALT ≤2.5 ULN and CEA within normal limits at time of randomization.

Patients (n=1987) were randomized to XELODA 1,250 mg/m^2 orally twice daily for the first 14 days of a 21-day cycle for a total of 8 cycles or fluorouracil 425 mg/m^2 and leucovorin 20 mg/m^2 intravenously on days 1 to 5 of each 28-day cycle for a total of 6 cycles. The XELODA dose was reduced in patients with baseline CLcr of 30 to 50 mL/min. The major efficacy outcome measure was disease-free survival (DFS).

The baseline demographics are shown in Table 9. The baseline characteristics were well-balanced between arms.

Table 9 Baseline Demographics in X-ACT
 | XELODA (N=1004) | Fluorouracil + Leucovorin (N=983)
Age (median, years) | 62 | 63
Range | (25-80) | (22-82)
Sex
Male, % | 54 | 54
Female, % | 46 | 46
ECOG Performance Status
0, % | 85 | 85
1, % | 15 | 15
Staging – Primary Tumor
PT1, % | 1 | 0.6
PT2, % | 9 | 9
PT3, % | 76 | 76
PT4, % | 14 | 0
Other, % | 0.1 | 14
Staging – Lymph Node
pN1, % | 69 | 71
pN2, % | 30 | 29
Other, % | 0.4 | 0.1

Efficacy results are summarized in Table 10 and Figures 1 and 2. The median follow-up at the time of the analysis was 6.9 years. Because the upper 2-sided 95% confidence limit of hazard ratio for DFS was less than 1.20, XELODA was non-inferior to fluorouracil + leucovorin. The choice of the non-inferiority margin of 1.20 corresponds to the retention of approximately 75% of the fluorouracil + leucovorin effect on DFS. The hazard ratio for XELODA compared to fluorouracil + leucovorin with respect to overall survival was 0.86 (95% CI 0.74, 1.01). The 5-year overall survival rates were 71% for XELODA and 68% for fluorouracil + leucovorin.

Table 10 Efficacy Results in X-ACT * (All Randomized Population)
Efficacy Parameters | XELODA (N=1004) | Fluorouracil + Leucovorin (N=983)
5-year Disease-free Survival Rate † | 59% | 55%
Hazard Ratio | 0.88
(95% CI) | (0.77, 1.01)
p-value * | p = 0.068

Figure 1 Kaplan-Meier Estimates of Disease-Free Survival in X-ACT (All Randomized Population)

Figure 2 Kaplan-Meier Estimates of Overall Survival in X-ACT (All Randomized Population)

In Combination with Oxaliplatin-Containing Regimens

The efficacy of XELODA in combination with oxaliplatin for the adjuvant treatment of patients with Stage III colon cancer as a component of a combination chemotherapy regimen was derived from studies in the published literature, including NO16968 [NCT00069121], a multicenter, open-label, randomized trial, where the major efficacy outcome measure was disease free survival.

Perioperative Treatment of Rectal Cancer

The efficacy of XELODA for the perioperative treatment of adults with locally advanced rectal cancer as a component of chemoradiotherapy was derived from studies in the published literature, including Rektum-III [NCT01500993], a randomized, open-label, multicenter, non-inferiority trial, where the major efficacy outcome measure was overall survival.

Metastatic Colorectal Cancer

The efficacy of XELODA as a single agent was evaluated in two open-label, multicenter, randomized, controlled clinical trials (Study SO14695 and Study SO14796). Eligible patients received first-line treatment for metastatic colorectal cancer. Patients were randomized to XELODA 1,250 mg/m^2 twice daily for first 14 days of a 21-day cycle or leucovorin 20 mg/m^2 intravenously followed by fluorouracil 425 mg/m^2 as an intravenous bolus on days 1 to 5 of each 28-day cycle.

The efficacy outcome measures were overall survival, time to progression and response rate (complete plus partial responses). Responses were defined by the World Health Organization criteria and submitted to a blinded independent review committee (IRC). Differences in assessments between the investigator and IRC were reconciled by the sponsor, blinded to treatment arm, according to a specified algorithm. Survival was assessed based on a non-inferiority analysis.

The baseline demographics are shown in Table 11.

Table 11 Baseline Demographics for Study SO14695 and Study SO14796
 | Study SO14695 |  | Study SO14796
 | XELODA (N=302) | Fluorouracil + Leucovorin (N=303) | XELODA (N=301) | Fluorouracil + Leucovorin (N=301)
Age (median, years) | 64 | 63 | 64 | 64
Range | (23-86) | (24-87) | (29-84) | (36-86)
Sex
Male, % | 60 | 65 | 57 | 57
Female, % | 40 | 35 | 43 | 43
Karnofsky PS (median) | 90 | 90 | 90 | 90
Range | (70-100) | (70-100) | (70-100) | (70-100)
Colon, % | 74 | 77 | 66 | 65
Rectum, % | 26 | 23 | 34 | 35
Prior radiation therapy, % | 17 | 21 | 14 | 14
Prior adjuvant fluorouracil, % | 28 | 36 | 19 | 14

Efficacy results for Study SO14695 and Study SO14796 are shown in Table 12 and Table 13.

Table 12 Efficacy Results for First-Line Treatment of Metastatic Colorectal Cancer (Study SO14695)
 | XELODA (N=302) | Fluorouracil + Leucovorin (N=303)
Overall Response Rate
% (95% CI) | 21 (16, 26) | 11 (8, 15)
p-value | 0.0014
Time to Progression
Median, months (95% CI) | 4.2 (3.9, 4.5) | 4.3 (3.4, 5.0)
Hazard Ratio | 0.99
95% CI | (0.84, 1.17)
Overall Survival
Median, months (95% CI) | 12.5 (10.5, 14.3) | 13.4 (12.0, 14.7)
Hazard Ratio | 1.00
95% CI | (0.84, 1.18)

Table 13 Efficacy Results for First-Line Treatment of Metastatic Colorectal Cancer (Study SO14796)
 | XELODA (N=301) | Fluorouracil + Leucovorin (N=301)
Overall Response Rate
% (95% CI) | 21 (16, 26) | 14 (10, 18)
p-value | 0.027
Time to Progression
Median, months (95% CI) | 4.5 (4.2, 5.5) | 4.3 (3.4, 5.1)
Hazard Ratio | 0.97
95% CI | (0.82, 1.14)
Overall Survival
Median, months (95% CI) | 13.3 (12.1, 14.8) | 12.1 (11.1,14.1)
Hazard Ratio | 0.92
95% CI | (0.78, 1.09)

Efficacy results of the pooled population from Study SO14695 and Study SO14796 are shown in Figure 3. Statistical analyses were performed to determine the percent of the survival effect of fluorouracil + leucovorin that was retained by XELODA. The estimate of the survival effect of fluorouracil + leucovorin was derived from a meta-analysis of ten randomized studies from the published literature comparing fluorouracil to regimens of fluorouracil + leucovorin that were similar to the control arms used in these Studies SO14695 and SO14796. The method for comparing the treatments was to examine the worst case (95% confidence upper bound) for the difference between fluorouracil + leucovorin and XELODA, and to show that loss of more than 50% of the fluorouracil + leucovorin survival effect was ruled out. It was demonstrated that the percent of the survival effect of fluorouracil + leucovorin maintained was at least 61% for Study SO14796 and 10% for Study SO14695. The pooled result is consistent with a retention of at least 50% of the effect of fluorouracil + leucovorin. It should be noted that these values for preserved effect are based on the upper bound of the fluorouracil + leucovorin vs XELODA difference.

Figure 3 Kaplan-Meier Curve for Overall Survival of Pooled Data (Studies SO14695 and SO14796)

In Combination with Oxaliplatin

The efficacy of XELODA for the treatment of patients with unresectable or metastatic colorectal cancer as a component of a combination chemotherapy regimen was derived from studies in the published literature, including NO16966 [NCT00069095], a randomized, non-inferiority, 2×2 factorial trial, where the major efficacy outcome measure was progression free survival.

14.2 Metastatic Breast Cancer

In Combination With Docetaxel

The efficacy of XELODA in combination with docetaxel was evaluated in an open-label, multicenter, randomized trial (Study SO14999). Eligible patients had metastatic breast cancer resistant to, or recurring during or after an anthracycline-containing therapy, or relapsing during or recurring within 2 years of completing an anthracycline-containing adjuvant therapy were enrolled. Patients were randomized to XELODA 1,250 mg/m^2 twice daily for the first 14 days of a 21-day cycle and docetaxel 75 mg/m^2 as a 1-hour intravenous infusion on day 1 of day of a 21-day cycle or docetaxel 100 mg/m^2 as a 1-hour intravenous infusion on day 1 of a 21-day cycle. The efficacy outcome measures were time to disease progression, overall survival, and response rate.

Patient demographics are provided in Table 14.

Table 14 Baseline Demographics in Metastatic Breast Cancer (Study SO14999)
 | XELODA + Docetaxel (N=255) | Docetaxel (N=256)
Age (median, years) | 52 | 51
Karnofsky Performance Status (median) | 90 | 90
Site of Disease
Lymph nodes, % | 47 | 49
Liver, % | 45 | 48
Bone, % | 42 | 46
Lung, % | 37 | 39
Skin, % | 29 | 29
Prior Chemotherapy
Anthracycline*, % | 100 | 100
Fluorouracil, % | 77 | 74
Paclitaxel, % | 10 | 9
Resistance to an Anthracycline
No resistance, % | 7 | 7
Progression on anthracycline therapy, % | 26 | 29
Stable disease after 4 cycles of anthracycline therapy, % | 16 | 16
Relapsed within 2 years of completion of anthracycline-adjuvant therapy, % | 31 | 29
Experienced a brief response to anthracycline therapy, with subsequent progression while on therapy or within 12 months after last dose, % | 20 | 20
No. of Prior Chemotherapy Regimens for Treatment of Metastatic Disease
0, % | 35 | 31
1, % | 48 | 53
2, % | 17 | 15
3, % | 0 | 1

Efficacy results are shown in Table 15, Figure 4 and Figure 5.

Table 15 Efficacy Results in Metastatic Breast Cancer (Study SO14999)
Efficacy Parameter | XELODA + Docetaxel (N=255) | Docetaxel (N=256)
Time to Disease Progression
Median, months | 6.1 | 4.2
95% CI | (5.4, 6.5) | (3.5, 4.5)
Hazard Ratio | 0.643
p-value | 0.0001
Overall Survival
Median, months | 14.5 | 11.6
95% CI | (12.3, 16.3) | (9.8, 12.7)
Hazard Ratio | 0.775
p-value | 0.0126
Response Rate* | 32% | 22%

Figure 4 Kaplan-Meier Estimates for Time to Disease Progression in Metastatic Breast Cancer (Study SO14999)

Figure 5 Kaplan-Meier Estimates of Survival in Metastatic Breast Cancer (Study SO14999)

Single Agent

The efficacy of XELODA as a single agent was evaluated in an open-label single-arm trial (Study SO14697). Eligible patients had metastatic breast cancer resistant to both paclitaxel and an anthracycline-containing chemotherapy regimen or resistant to paclitaxel and for whom further anthracycline therapy is not indicated (e.g., patients who have received cumulative doses of 400 mg/m^2 of doxorubicin or doxorubicin equivalents). Resistance was defined as progressive disease while on treatment, with or without an initial response, or relapse within 6 months of completing treatment with an anthracycline-containing adjuvant chemotherapy regimen. Patients received XELODA 1,255 mg/m^2 orally twice daily for first 14-days of a 21-day treatment cycle. The major efficacy outcome measure was tumor response rate in patients with measurable disease, with response defined as a 50% decrease in sum of the products of the perpendicular diameters of bidimensionally measurable disease for at least 1 month.

The baseline demographics are shown in Table 16.

Table 16 Baseline Demographics in Metastatic Breast Cancer (Study SO14697)
 | Patients With; Measurable Disease; (N=135) | All Patients; (N=162)
Age (median, years) | 55 | 56
Karnofsky Performance Status | 90 | 90
No. Disease Status
1-2, % | 32 | 37
3-4, % | 46 | 43
>5, % | 22 | 21
Dominant Site of Disease
Visceral*, % | 75 | 68
Soft Tissue, % | 22 | 22
Bone, % | 3 | 10
Prior Chemotherapy
Paclitaxel, % | 100 | 100
Anthracycline†, % | 90 | 91
Fluorouracil, % | 81 | 82
Resistance to Paclitaxel, % | 76 | 77
Resistance to an Anthracycline†, % | 41 | 41
Resistance to both Paclitaxel and an Anthracycline†, % | 32 | 31
* Lung, pleura, liver, peritoneum
† Includes 2 patients treated with an anthracenedione

Efficacy for Study SO14697 are shown in Table 17.

Table 17 Efficacy Results in Metastatic Breast Cancer (Study SO14697)
Efficacy Parameter | Resistance to Both Paclitaxel and an; Anthracycline; (N=43)
Response Rate* | 25.6%
(95% CI) | (13.5, 41.2)
Complet Response | 0%
Partial Response* | 11%
Duration of Response*
Median, months (Range) | 5.1 (2.1-7.7)
* Includes 2 patients treated with an anthracenedione
† From date of first response

For the subgroup of 43 patients who were doubly resistant, the median time to progression was 3.4 months and the median survival was 8.4 months. The objective response rate in this population was supported by a response rate of 18.5% (1 CR, 24 PRs) in the overall population of 135 patients with measurable disease, who were less resistant to chemotherapy (see Table 15). The median time to progression was 3.0 months and the median survival was 10.1 months.

14.3 Gastric, Esophageal, or Gastroesophageal Junction Cancer

The efficacy of XELODA for treatment of adults with unresectable or metastatic gastric, esophageal, or gastroesophageal junction cancer as a component of a combination chemotherapy regimen was derived from studies in the published literature. XELODA was evaluated in REAL-2, a randomized non-inferiority, 2×2 factorial trial, where the major efficacy outcome measure was overall survival, and an additional randomized trial conducted by the North Central Cancer Treatment Group, where the major efficacy outcome measure was objective response rate.

The efficacy of XELODA for the treatment of adults with HER2-overexpressing metastatic gastric or gastroesophageal junction adenocarcinoma who have not received prior treatment for metastatic disease as a component of a combination regimen was derived from studies in the published literature. XELODA was evaluated in the ToGA trial [NCT01041404], an open-label, multicenter, randomized trial where the primary efficacy measure was overall survival.

14.4 Pancreatic Cancer

The efficacy of XELODA for the adjuvant treatment of adults with pancreatic adenocarcinoma as a component of a combination chemotherapy regimen was derived from a study in the published literature. XELODA was evaluated in ESPAC-4 trial, a two-group, open-label, multicenter, randomized trial, where the major efficacy outcome measure was overall survival.

15 REFERENCES

1. "OSHA Hazardous Drugs." OSHA. http://www.osha.gov/SLTC/hazardousdrugs/index.html.

16 HOW SUPPLIED/STORAGE AND HANDLING

XELODA (capecitabine) tablets are supplied as follows:

- 150 mg, biconvex, oblong, film-coated, light peach tablets with "XELODA" on one side and "150" on the other; available in bottles of 60 tablets (NDC 61269-470-60), individually packaged in a carton.
- 500 mg, biconvex, oblong, film-coated, peach tablets with "XELODA" on one side and "500" on the other; available in bottles of 120 tablets (NDC 61269-475-12), individually packaged in a carton.

Storage and Handling

Store at 20° to 25°C (68° to 77°F); excursions permitted to 15° to 30°C (59° to 86°F) [see USP Controlled Room Temperature]. KEEP TIGHTLY CLOSED.

XELODA is a hazardous drug. Follow applicable special handling and disposal procedures.^1

17 PATIENT COUNSELING INFORMATION

Advise the patient to read the FDA-approved patient labeling (Patient Information).

Serious Adverse Reactions or Death from Dihydropyrimidine Dehydrogenase (DPD) Deficiency

Prior to initiating XELODA treatment, inform patients of the potential for serious or fatal adverse reactions due to DPD deficiency and testing for genetic variants of DPYD. Advise patients to immediately contact their healthcare provider if symptoms of severe mucositis, diarrhea, neutropenia, and neurotoxicity occur [see Warnings and Precautions (5.1)and Clinical Pharmacology (12.5)].

Increased Risk of Bleeding with Concomitant Use of Vitamin K Antagonists

Advise patients on vitamin K antagonists, such as warfarin, that they are at an increased risk of severe bleeding while taking XELODA. Advise these patients that INR should be monitored more frequently, and dosage modifications of the vitamin K antagonist may be required, while taking and after discontinuation of XELODA. Advise these patients to immediately contact their healthcare provider if signs or symptoms of bleeding occur [see Warnings and Precautions (5.2)].

Cardiotoxicity

Advise patients of the risk of cardiotoxicity and to immediately contact their healthcare provider for new onset of chest pain, shortness of breath, dizziness, or lightheadedness [see Warnings and Precautions (5.3)].

Diarrhea

Inform patients experiencing grade 2 diarrhea (an increase of 4 to 6 stools/day or nocturnal stools) or greater or experiencing severe bloody diarrhea with severe abdominal pain and fever to stop taking XELODA. Advise patients on the use of antidiarrheal treatments (e.g., loperamide) to manage diarrhea [see Warnings and Precautions (5.4)].

Dehydration

Instruct patients experiencing grade 2 or higher dehydration to stop taking XELODA immediately and to contact their healthcare provider. Advise patients to not restart XELODA until rehydrated and any precipitating causes have been corrected or controlled [see Warnings and Precautions (5.5)].

Renal Toxicity

Instruct patients experiencing decreased urinary output or other signs and symptoms of renal toxicity to immediately contact their healthcare provider [see Warnings and Precautions (5.6)].

Serious Skin Toxicities

Instruct patients skin rash, blistering, or peeling to immediately contact their healthcare provider [see Warnings and Precautions (5.7)].

Palmar-Plantar Erythrodysesthesia Syndrome

Instruct patients experiencing grade 2 palmar-plantar erythrodysesthesia syndrome or greater to stop taking XELODA immediately and to contact their healthcare provider. Inform patients that initiation of symptomatic treatment is recommended and hand-and-foot syndrome can lead to loss of fingerprints which could impact personal identification [see Warnings and Precautions (5.8)].

Myelosuppression

Inform patients who develop a fever of 100.5°F or greater or other evidence of potential infection to immediately contact their healthcare provider [see Warnings and Precautions (5.9)].

Hyperbilirubinemia

Inform patients who develop jaundice or icterus to immediately contact their healthcare provider [see Warnings and Precautions (5.10)].

Embryo-Fetal Toxicity

Advise pregnant women and females of reproductive potential of the potential risk to a fetus. Advise females of reproductive potential to inform their healthcare provider of a known or suspected pregnancy [see Warnings and Precautions (5.11), Use in Specific Populations (8.1)].

Advise females of reproductive potential to use effective contraception during treatment with XELODA and for 6 months after the last dose [see Use in Specific Populations (8.3)].

Advise males with female partners of reproductive potential to use effective contraception during treatment with XELODA and for 3 months after the last dose [see Use in Specific Populations (8.3)].

Lactation

Advise females not to breastfeed during treatment with XELODA and for 1 week after the last dose [see Use in Specific Populations (8.2)].

Infertility

Advise males and females of reproductive potential that XELODA may impair fertility [see Use in Specific Populations (8.3)].

Hypersensitivity and Angioedema

Advise patients that XELODA may cause severe hypersensitivity reactions and angioedema.

Advise patients who have known hypersensitivity to capecitabine or 5-fluorouracil to inform their healthcare provider [see Contraindications (4)]. Instruct patients who develop hypersensitivity reactions or mucocutaneous symptoms (e.g., urticaria, rash, erythema, pruritus, or swelling of the face, lips, tongue or throat which make it difficult to swallow or breathe) to stop taking XELODA and immediately contact their healthcare provider or to go to an emergency room. [see Adverse Reactions (6)].

Nausea and Vomiting

Instruct patients experiencing grade 2 nausea (food intake significantly decreased but able to eat intermittently) or greater to stop taking XELODA and to immediately contact their healthcare provider for management of nausea [see Adverse Reactions (6.1)].

Instruct patients experiencing grade 2 vomiting (2 to 5 episodes in a 24-hour period) or greater to stop taking XELODA immediately and to contact their healthcare provider for management of vomiting [see Adverse Reactions (6.1)].

Stomatitis

Inform patients experiencing grade 2 stomatitis (painful erythema, edema or ulcers of the mouth or tongue, but able to eat) or greater to stop taking XELODA immediately and to contact their healthcare provider [see Adverse Reactions (6.1)].

Important Administration Instructions

Advise patients to swallow XELODA tablets whole with water within 30 minutes after a meal. Advise patients and caregivers not to chew, crush, or cut XELODA tablets. Advise patients if they cannot swallow XELODA tablets whole to inform their healthcare provider [see Dosage and Administration (2.7), Warnings and Precautions (5.12)].

Drug interactions

Instruct patients not to take products containing folic acid or folate analog products (e.g., leucovorin, levoleucovorin) unless directed to do so by their healthcare provider. Advise patients to inform their healthcare provider of all prescription or nonprescription medications, vitamins or herbal products [see Drug Interactions (7.1, 7.2, 7.3)].

Distributed by:

H2-Pharma, LLC
Montgomery, AL 36117, USA

Licensed by:
CHEPLAPHARM Arzneimittel GmbH
Ziegelhof 24, 17489 Greifswald, Germany

XELODA® is a registered trademark of CHEPLAPHARM Arzneimittel GmbH.
© 2025 CHEPLAPHARM Arzneimittel GmbH. All rights reserved.

Patient Information
XELODA® (zeh-LOE-duh)
(capecitabine)
tablets

What is the most important information I should know about XELODA?

XELODA can cause serious side effects, including:

- Serious side effects or death in people with dihydropyrimidine dehydrogenase (DPD) enzyme deficiency.

- People with certain changes in a gene called DPYD may have a deficiency of the DPD enzyme.
- People who do not have any DPD enzyme are at increased risk of sudden side effects that come on early during treatment with XELODA and can be serious, and sometimes lead to death.
- People who have some DPD enzyme may have an increased risk of serious side effects or death with XELODA treatment.
- Your healthcare provider will test you for DPYD before starting treatment with XELODA, unless you need treatment right away.

Call your healthcare provider right away if you develop any of the following symptoms and they are severe, including:

- sores of the mouth, tongue, throat and esophagus

- trouble walking, or problems woth balance or coordination

- diarrhea

- changes in mood or mental status

- fever, chills, cough, or any other signs of infection

- problems with thinking, concentration, memory, or sleep

- Increased risk of bleeding when taking XELODA with blood thinner medicines, such as warfarin. Taking XELODA with these medicines can cause changes in how fast your blood clots and can cause bleeding that can lead to death. This can happen as soon as a few days after you start taking XELODA, or later during treatment, and possibly within 1 month after you stop taking XELODA. This can happen in people whose cancer has spread to the liver (liver metastasis) andin people whose cancer has not spread to the liver.
  - Before taking XELODA, tell your healthcare provider if you are taking warfarin or another blood thinner medicine.
  - If you take warfarin or another blood thinner that is like warfarin during treatment with XELODA, your healthcare provider should do blood tests more often, to check how fast your blood clots during and after you stop treatment with XELODA. Your healthcare provider may change your dose of the blood thinner medicine if needed.
  - Tell your healthcare provider right away if you develop any signs or symptoms of bleeding.

See "What are the possible side effects of XELODA?" for more information about side effects.

What is XELODA?

XELODA is a prescription medicine used to treat:

- A kind of cancer called colon or rectal (colorectal) cancer. XELODA may be used:
  - alone or in combination with other chemotherapy medicines in people with colon cancer that has spread to lymph nodes in the area close to the colon (Stage III colon cancer), to help prevent your cancer from coming back after you have had surgery.
  - adults with rectal cancer, around the time of your surgery, as a part of chemotherapy and radiation (chemoradiation) treatment when your rectal cancer has spread to nearby tissues (locally advanced).
  - alone or in combination with other chemotherapy medicines, when your colorectal cancer cannot be removed by surgery or has spread to other areas of your body (metastatic).

- A kind of cancer called breast cancer. XELODA may be used in people with breast cancer that is advanced or has spread to other parts of the body (metastatic):
  - alone if you are not able to receive an anthracycline medicine or taxane-containing chemotherapy.
  - in combination with docetaxel when you have received anthracycline containing chemotherapy and it is no longer working.

- Kinds of cancer called stomach (gastric), esophageal, or gastroesophageal junction (GEJ) cancer. XELODA may be used in adults:
  - in combination with other chemotherapy medicines when your cancer of the stomach, esophagus, or GEJ cannot be removed by surgery or has spread to other parts of the body (metastatic).
  - when your cancer of the stomach, esophagus, or GEJ is metastatic adenocarcinoma, and:
    - is HER2-positive, and
    - you have not received treatment with XELODA in combination with other treatments for your metastatic cancer.

- A kind of cancer called pancreatic cancer. XELODA may be used to treat adults in combination with other chemotherapy medicines, to help prevent your pancreatic cancer from coming back after you have had surgery.

It is not known if XELODA is safe and effective in children.

Do not take XELODA if you:

- have had a severe allergic reaction to fluorouracil or capecitabine. See the end of this leaflet for a complete list of ingredients in XELODA.

Talk to your healthcare provider before taking XELODA if you are not sure.

Before taking XELODA, tell your healthcare provider about all your medical conditions, including if you:

See "What is the most important information I should know about XELODA?"

- have had heart problems.
- have kidney or liver problems.
- are pregnant or plan to become pregnant. XELODA can harm your unborn baby.
  Females who are able to become pregnant:
  - Your healthcare provider should do a pregnancy test before you start treatment with XELODA.
  - Use an effective method of birth control (contraception) during treatment and for 6 months after your last dose of XELODA. Talk to your healthcare provider about birth control choices that may be right for you during treatment with XELODA.
  - Tell your healthcare provider right away if you become pregnant or think you might be pregnant during treatment with XELODA.
  Males who have female partners who are able to become pregnant should use effective birth control during treatment and for 3 months after your last dose of XELODA.
- are breastfeeding or plan to breastfeed. It is not known if XELODA passes into your breast milk. Do not breastfeed during treatment with XELODA and for 1 week after your last dose of XELODA.

Tell your healthcare provider about all the medicines you take, including prescription and over-the-counter medicines, vitamins, and herbal supplements. XELODA may affect the way other medicines work, and other medicines may affect the way XELODA works.

How should I take XELODA?

- Take XELODA exactly as your healthcare provider tells you to take it.
- Your healthcare provider will tell you how much XELODA to take and when to take it. The number of days that you will take XELODA during each treatment cycle and the number of days in each treatment cycle depends on the type of cancer you are being treated for.
- Take XELODA 2 times a day at the same time each day, about 12 hours apart.
- Take XELODA within 30 minutes after finishing a meal.
- Swallow XELODA tablets whole with water. Do not chew, cut, or crush XELODA tablets. See "Eye irritation, skin rash and other side effects with exposure to crushed XELODA tablets" in the section called "What are the possible side effects of XELODA?"
- If you cannot swallow XELODA tablets whole, tell your healthcare provider.
- Your healthcare provider may change your dose, temporarily stop, or permanently stop treatment with XELODA if you develop side effects.
- Do not take products that contain folic acid or folate analog products, for example, leucovorin or levoleucovorin, during treatment with XELODA, unless your healthcare provider instructs you to take it.
- If you vomit after taking a dose of XELODA, do not take another dose at that time. Wait and take your next dose of XELODA at your scheduled time.
- If you miss a dose of XELODA, just skip the dose and then take your next dose at your scheduled time.
- If you take too much XELODA, call your healthcare provider or go to the nearest hospital emergency room right away.

What are the possible side effects of XELODA?

XELODA can cause serious side effects including:

- See "What is the most important information I should know about XELODA?"

- Heart problems. XELODA can cause heart problems including: heart attack and decreased blood flow to the heart, chest pain, irregular heartbeats, changes in the electrical activity of your heart seen on an electrocardiogram (ECG), problems with your heart muscle, heart failure, and sudden death. You may have an increased risk of heart problems with XELODA if you have a history of narrowing or blockage of the coronary arteries (coronary artery disease). Stop taking XELODA and call your healthcare provider or go to the nearest hospital emergency room right away if you get any new symptoms of a heart problem including:

- chest pain
- shortness of breath

- dizziness
- lightheadedness

- Diarrhea. Diarrhea is common with XELODA and can sometimes be severe. Stop taking XELODA and call your healthcare provider right away if the number of bowel movements you have in a day increases by 4 or more bowel movements than what is usual for you, or if you have bowel movements at night. Ask your healthcare provider about what medicines you can take to treat your diarrhea. Stop taking XELODA if you have severe bloody diarrhea with severe abdominal pain and fever and call you healthcare provider right away.
- Loss of too much body fluid (dehydration) and kidney failure. Dehydration can happen with XELODA and may affect how well your kidneys work. If you take XELODA with certain other medicines that can cause kidney problems, you may have an increased risk of serious kidney failure that can sometimes lead to death. Your risk of kidney failure may also be increased if you have kidney problems before taking XELODA.
  Nausea, and vomiting are common with XELODA. If you lose your appetite, feel weak, and have nausea, vomiting, or diarrhea, you can quickly become dehydrated.
  Stop taking XELODA and call your healthcare provider right away if you:
  - vomit 2 or more times in a day.
  - are only able to eat or drink a little now and then, or not at all due to nausea.
  - have diarrhea. See "diarrhea" above.
  You may need to receive fluids through your vein (intravenous) to treat your dehydration or receive treatment for kidney failure.
- Severe skin and mouth reactions.
  - XELODA can cause severe skin reactions that may lead to death. Tell your healthcare provider right away if you develop a skin rash, blister and peeling of your skin. Your healthcare provider may tell you to stop taking XELODA if you have a serious skin reaction. Do not take XELODA again if this happens.
  - XELODA can also cause "hand and foot" syndrome. Hand and foot syndrome is common with XELODA and can cause you to have numbness and changes in sensation in your hands and feet, or cause redness, pain, swelling of your hands and feet. Stop taking XELODA and call your healthcare provider right away if you have any of these symptoms and you are not able to do your usual activities.
  - Hand and foot syndrome can lead to a loss of fingerprints which could impact your identification.
  - You may get sores in your mouth or on your tongue when taking XELODA. Stop taking XELODA and call your healthcare provider right away if you get painful redness, swelling, or ulcers in your mouth or tongue, or if you are having problems eating.
- Decreased white blood cells, platelets, and red blood cell counts. Decreased white blood cells, platelets, and red blood cell counts can happen with XELODA and can sometimes be severe. Your healthcare provider will do blood tests during treatment with XELODA to check your blood cell counts.
  If your white blood cell count is very low, you are at increased risk for infection. Call your healthcare provider right away if you develop a fever of 100.5°F or greater or have other signs and symptoms of infection.
- Increased level of bilirubin in your blood and liver problems. Increased bilirubin in your blood is common with XELODA and can also sometimes be severe. Your healthcare provider will check you for these problems during treatment with XELODA. Tell your healthcare provider right away if you develop yellowing of your skin or the white part of your eyes.
- Eye irritation, skin rash and other side effects with exposure to crushed XELODA tablets. If you come into contact with (you are exposed to) crushed XELODA tablets, you may develop side effects including:

- eye irritation and swelling
- skin rash
- diarrhea

- feeling like pins and needles in your hands
- headache
- stomach irritation
- nausea and vomiting

Do not chew, cut, or crush XELODA tablets. See "How should I take XELODA tablets."
If for any reason your tablets must be cut or crushed, this must be done by your pharmacist or healthcare provider.

Your healthcare provider may decide to decrease your dose, or temporarily or permanently stop XELODA if you have serious side effects with XELODA.

The most common side effects in people with colon cancer who take XELODA alone to help prevent it from coming back include: hand and foot syndrome, diarrhea, and nausea.

The most common side effects in people with metastatic colorectal carcinoma who take XELODA alone include:

- decreased red blood cell count
- diarrhea
- hand and foot syndrome
- increased bilirubin level in your blood

- nausea
- tiredness
- stomach-area (abdominal) pain

The most common side effects in people with metastatic breast cancer who take XELODA in combination with docetaxel include:

- diarrhea
- mouth sores or mouth inflammation
- hand and foot syndrome
- nausea and vomiting

- hair loss
- swelling
- stomach-area (abdominal) pain

The most common side effects in people with metastatic breast cancer who take XELODA alone include:

- decreased white blood cell and red blood cell count
- diarrhea
- hand and foot syndrome

- nausea and vomiting
- tiredness
- skin inflammation, including rash

Severe allergic reactions can happen with XELODA. See "Do not take XELODA if you:" Stop taking XELODA and call your healthcare provider right away or go to an emergency room if you have any of the following symptoms of a severe allergic reaction to XELODA:

- red itchy welts on your skin (hives)
- rash

- skin redness
- itching

- swelling of your face, lips, tongue or throat
- trouble swallowing or breathing

XELODA may cause fertility problems in females and males. This may affect the ability to have a child. Talk to your healthcare provider if you have concerns about fertility.

These are not all the possible side effects of XELODA.

Call your doctor for medical advice about side effects. You may report side effects to FDA at 1-800-FDA-1088.

How should I store XELODA?

- Store XELODA at room temperature between 68°F to 77°F (20°C to 25°C).
- Keep XELODA in a tightly closed container.
- Ask your healthcare provider or pharmacist how to safely throw away any unused XELODA.

Keep XELODA and all medicines out of the reach of children.

General information about the safe and effective use of XELODA.

Medicines are sometimes prescribed for purposes other than those listed in a Patient Information leaflet. Do not use XELODA for a condition for which it was not prescribed. Do not give XELODA to other people, even if they have the same symptoms you have. It may harm them. You can ask your pharmacist or healthcare provider for information about XELODA that is written for health professionals.

What are the ingredients in XELODA?

Active ingredient: capecitabine

Inactive ingredients: anhydrous lactose, croscarmellose sodium, hydroxypropyl methylcellulose, microcrystalline cellulose, magnesium stearate and purified water. The peach or light peach film coating contains hydroxypropyl methylcellulose, talc, titanium dioxide, and synthetic yellow and red iron oxides.

Distributed by: H2-Pharma, LLC, Montgomery, AL 36117, USA.

Licensed by: CHEPLAPHARM Arzneimittel GmbH, Ziegelhof 24, 17489 Greifswald, Germany.

XELODA® is a registered trademark of CHEPLAPHARM Arzneimittel GmbH.© 2025 CHEPLAPHARM Arzneimittel GmbH. All rights reserved.

For more information call 1-866-995-4272.

This Patient Information has been approved by the U.S. Food and Drug Administration.

Revised: 10/2025

PRINCIPAL DISPLAY PANEL - 150 mg Tablet Bottle Carton

NDC 61269-470-60

Xeloda®
(capecitabine)
Tablets

150 mg

Each tablet contains 150 mg
capecitabine.

Rx only

Warning: Hazardous Drug

60 tablets

CHEPLAPHARM

PRINCIPAL DISPLAY PANEL - 500 mg Tablet Bottle Carton

NDC 61269-475-12

Xeloda®

(capecitabine)

Tablets

500 mg

Each tablet contains 500 mg

capecitabine.

Rx only

Warning: Hazardous Drug

120 tablets

CHEPLAPHARM